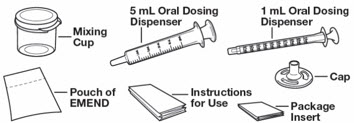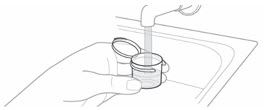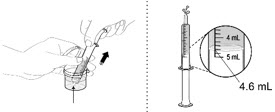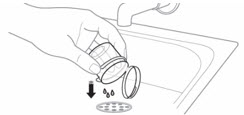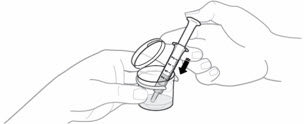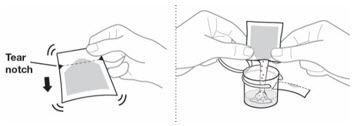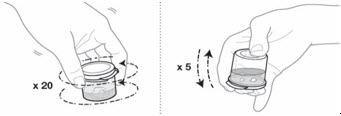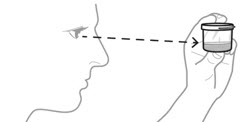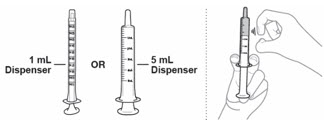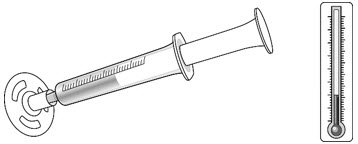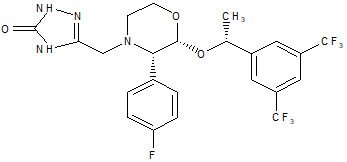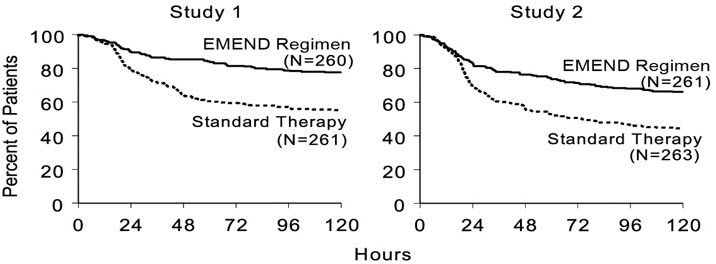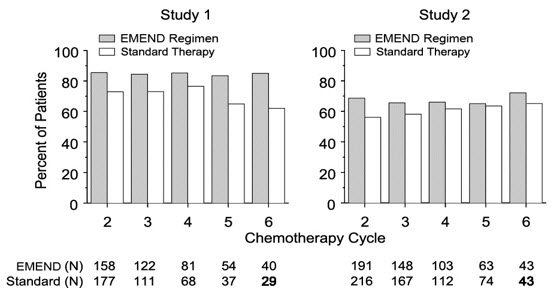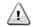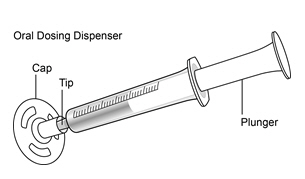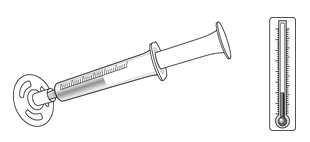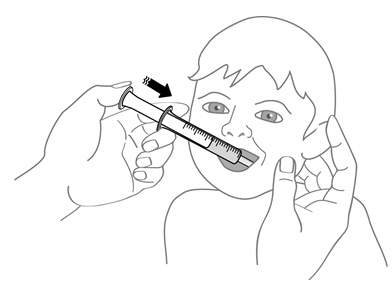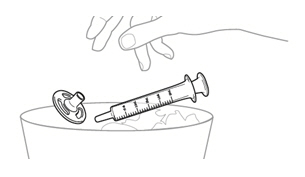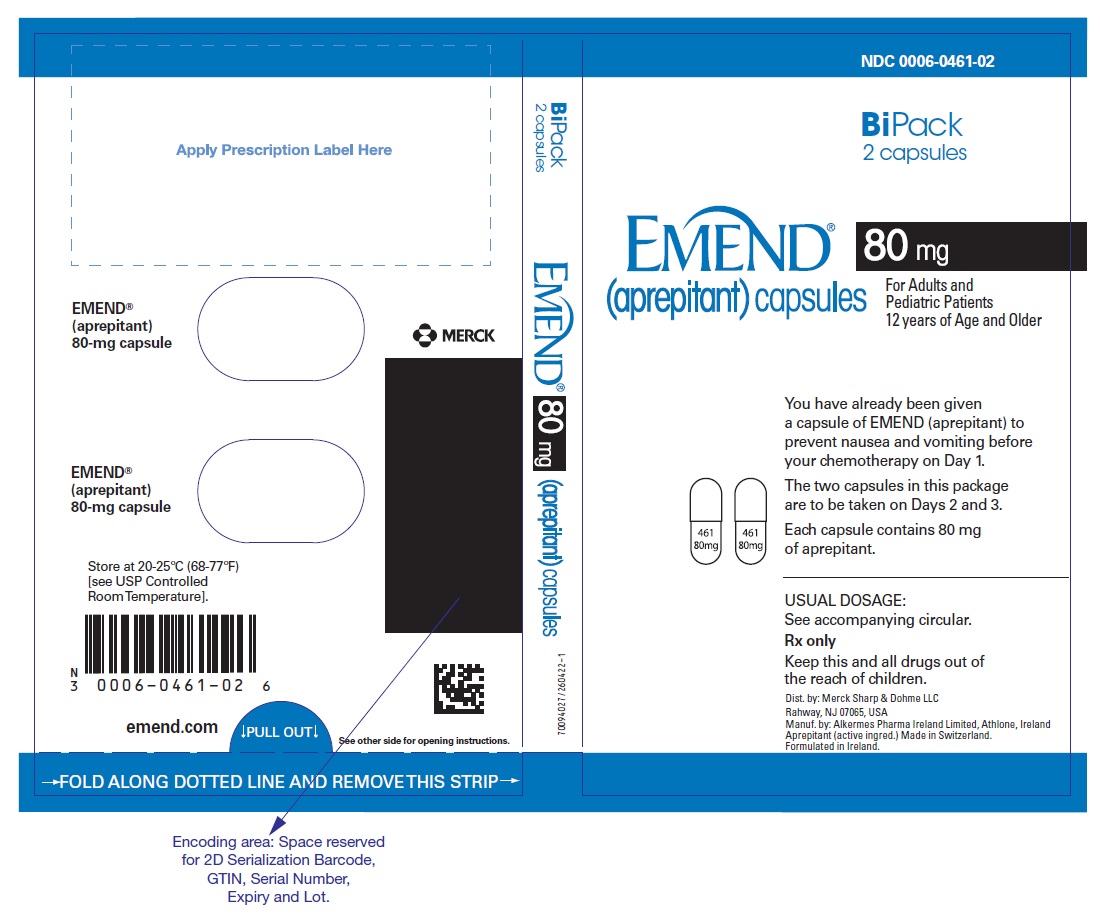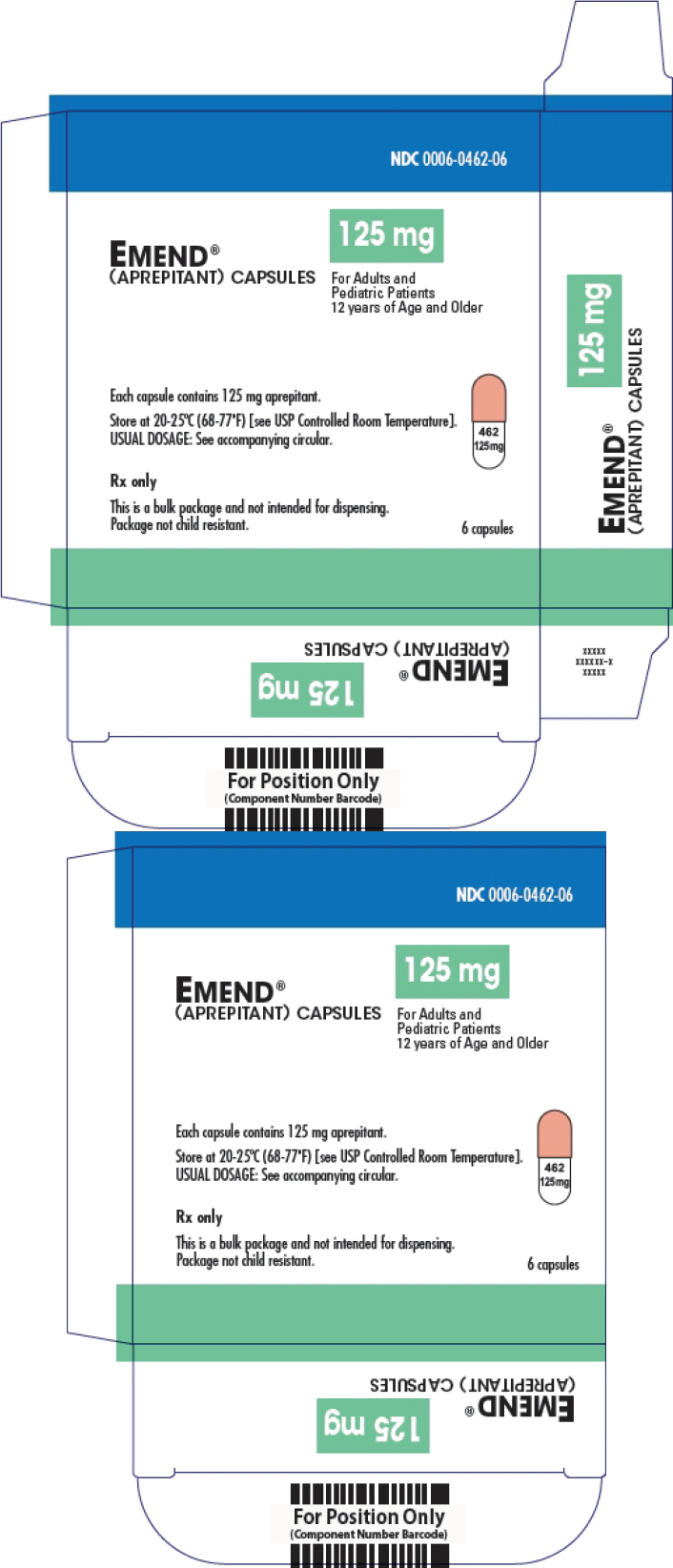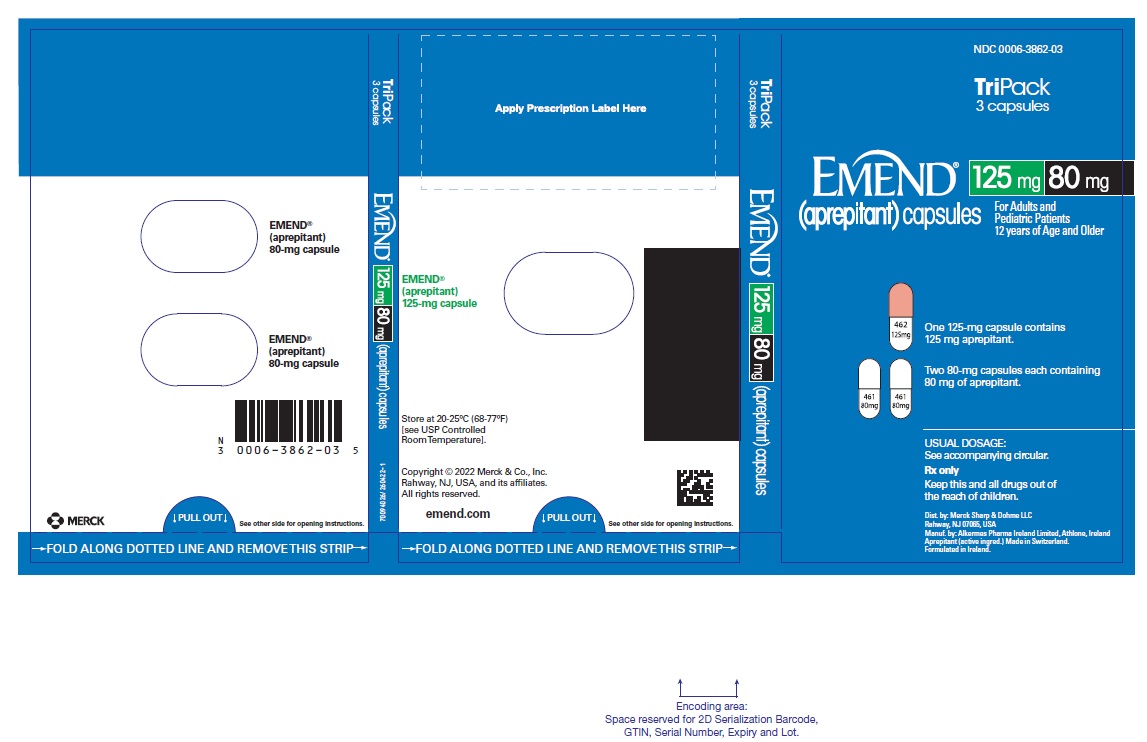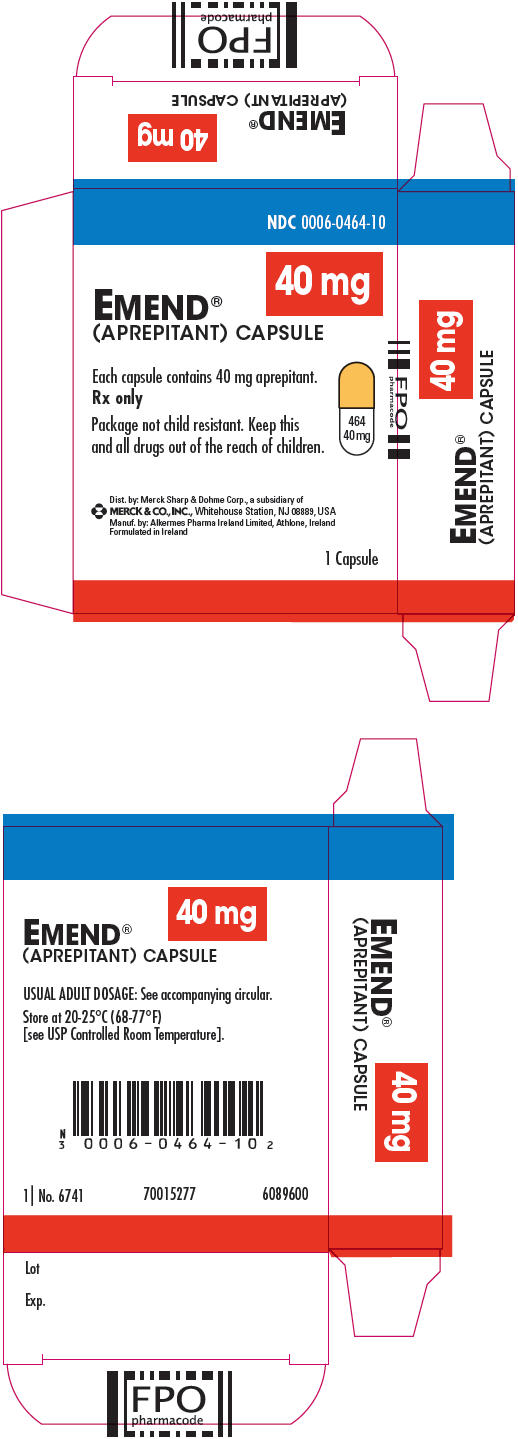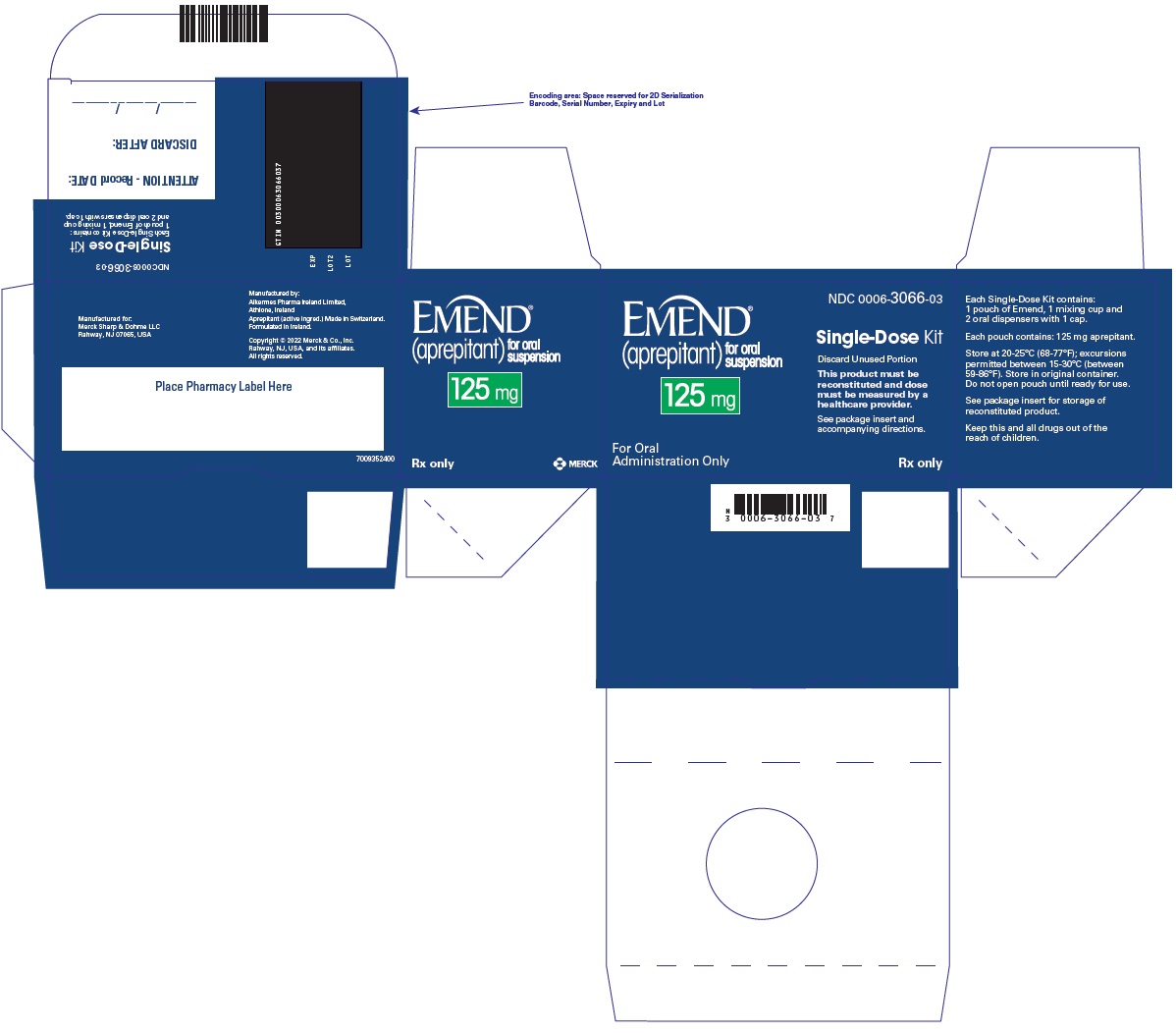 DRUG LABEL: EMEND
NDC: 0006-0461 | Form: CAPSULE
Manufacturer: Merck Sharp & Dohme LLC
Category: prescription | Type: HUMAN PRESCRIPTION DRUG LABEL
Date: 20240705

ACTIVE INGREDIENTS: aprepitant 80 mg/1 1
INACTIVE INGREDIENTS: sucrose; MICROCRYSTALLINE CELLULOSE; HYDROXYPROPYL CELLULOSE (1600000 WAMW); sodium lauryl sulfate; GELATIN, UNSPECIFIED; titanium dioxide; silicon dioxide

HIGHLIGHTS OF PRESCRIBING INFORMATION

These highlights do not include all the information needed to use EMEND CAPSULES and EMEND FOR ORAL SUSPENSION safely and effectively. See full prescribing information for EMEND CAPSULES and EMEND FOR ORAL SUSPENSION.
EMEND (aprepitant) capsules, for oral use
EMEND (aprepitant) for oral suspension
Initial U.S. Approval: 2003

1 INDICATIONS AND USAGE

EMEND® is a substance P/neurokinin 1 (NK1) receptor antagonist.

EMEND for oral suspension is indicated

- in combination with other antiemetic agents, in patients 6 months of age and older for prevention of:
  - acute and delayed nausea and vomiting associated with initial and repeat courses of highly emetogenic cancer chemotherapy (HEC) including high-dose cisplatin (1)
  - nausea and vomiting associated with initial and repeat courses of moderately emetogenic cancer chemotherapy (MEC) (1)

EMEND capsules is indicated

- in combination with other antiemetic agents, in patients 12 years of age and older for prevention of:
  - acute and delayed nausea and vomiting associated with initial and repeat courses of highly emetogenic cancer chemotherapy (HEC) including high-dose cisplatin (1)
  - nausea and vomiting associated with initial and repeat courses of moderately emetogenic cancer chemotherapy (MEC) (1)

Limitations of Use (1)

- EMEND has not been studied for treatment of established nausea and vomiting.
- Chronic continuous administration of EMEND is not recommended.

2 DOSAGE AND ADMINISTRATION

Recommended Dosage (2.1)

- EMEND capsules in adults and pediatric patients 12 years of age and older: is 125 mg on Day 1 and 80 mg on Days 2 and 3.
- EMEND for oral suspension in pediatric patients 6 months to less than 12 years of age or pediatric and adult patients unable to swallow capsules: see dosing recommendations in Table 3 in the Full Prescribing Information.
- Administer EMEND 1 hour prior to chemotherapy on Days 1, 2, and 3. If no chemotherapy is given on Days 2 and 3, administer EMEND in morning.
- See Full Prescribing Information for recommended dosages of concomitant dexamethasone and 5-HT3 antagonist for HEC and MEC.

Preparation and Administration (2.2, 2.3)

- EMEND capsules and EMEND for oral suspension can be administered with or without food.
- Swallow EMEND capsules whole.
- EMEND for oral suspension should be prepared by healthcare provider. Once prepared, it may be administered either by a healthcare provider, patient, or caregiver.
- For details on preparation see Full Prescribing Information.

3 DOSAGE FORMS AND STRENGTHS

EMEND capsules: 80 mg and 125 mg (3)

EMEND for oral suspension: 125 mg (3)

4 CONTRAINDICATIONS

- Known hypersensitivity to any component of this drug. (4)
- Concurrent use with pimozide. (4)

5 WARNINGS AND PRECAUTIONS

- CYP3A4 Interactions: Aprepitant is a substrate, weak-to-moderate inhibitor and inducer of CYP3A4; See Full Prescribing Information for recommendations regarding contraindications, risk of adverse reactions, and dosage adjustments of EMEND and concomitant drugs. (4, 5.1, 7.1, 7.2)
- Warfarin (a CYP2C9 substrate): Risk of decreased INR of prothrombin time; monitor INR in 2-week period, particularly at 7 to 10 days, following initiation of EMEND. (5.2, 7.1)
- Hormonal Contraceptives: Efficacy of contraceptives may be reduced during administration of and for 28 days following the last dose of EMEND. Use effective alternative or back-up methods of contraception. (5.3, 7.1, 8.3)

6 ADVERSE REACTIONS

Most common adverse reactions (≥3%) are (6.1):

- Adults: fatigue, diarrhea, asthenia, dyspepsia, abdominal pain, hiccups, white blood cell count decreased, dehydration, and alanine aminotransferase increased.
- Pediatrics: neutropenia, headache, diarrhea, decreased appetite, cough, fatigue, hemoglobin decreased, dizziness, and hiccups.

To report SUSPECTED ADVERSE REACTIONS, contact Merck Sharp & Dohme LLC at 1-877-888-4231 or FDA at 1-800-FDA-1088 or www.fda.gov/medwatch .

7 DRUG INTERACTIONS

See Full Prescribing Information for a list of clinically significant drug interactions. (4, 5.1, 5.2, 5.3, 7.1, 7.2)

FULL PRESCRIBING INFORMATION

1 INDICATIONS AND USAGE

EMEND® for oral suspension, in combination with other antiemetic agents, is indicated in patients 6 months of age and older for the prevention of:

- acute and delayed nausea and vomiting associated with initial and repeat courses of highly emetogenic cancer chemotherapy (HEC) including high-dose cisplatin.
- nausea and vomiting associated with initial and repeat courses of moderately emetogenic cancer chemotherapy (MEC).

EMEND® capsules, in combination with other antiemetic agents, is indicated in patients 12 years of age and older for the prevention of:

- acute and delayed nausea and vomiting associated with initial and repeat courses of highly emetogenic cancer chemotherapy (HEC) including high-dose cisplatin.
- nausea and vomiting associated with initial and repeat courses of moderately emetogenic cancer chemotherapy (MEC).

Limitations of Use

- EMEND has not been studied for the treatment of established nausea and vomiting.
- Chronic continuous administration of EMEND is not recommended because it has not been studied, and because the drug interaction profile may change during chronic continuous use.

2 DOSAGE AND ADMINISTRATION

2.1 Recommended Dosage

Adults and Pediatric Patients 12 Years of Age and Older

The recommended oral dosage of EMEND capsules, dexamethasone, and a 5-HT3 antagonist in adults and pediatric patients 12 years of age and older who can swallow oral capsules, for the prevention of nausea and vomiting associated with administration of HEC or MEC is shown in Table 1 or Table 2, respectively. For patients who cannot swallow oral capsules, EMEND for oral suspension can be used instead of EMEND capsules as shown in Table 3.

Table 1: Recommended Dosing for the Prevention of Nausea and Vomiting Associated with HEC
 | Population | Day 1 | Day 2 | Day 3 | Day 4
EMEND capsules [Administer EMEND capsules 1 hour prior to chemotherapy treatment on Days 1, 2, and 3. If no chemotherapy is given on Days 2 and 3, administer EMEND capsules in the morning.] | Adults and Pediatric Patients 12 Years and Older | 125 mg orally | 80 mg orally | 80 mg orally | none
Dexamethasone | Adults | 12 mg orally | 8 mg orally | 8 mg orally | 8 mg orally
Dexamethasone | Pediatric Patients 12 Years and Older | If a corticosteroid, such as dexamethasone, is co-administered, administer 50% of the recommended corticosteroid dose on Days 1 through 4 [see Clinical Studies (14.3)]. [Administer dexamethasone 30 minutes prior to chemotherapy treatment on Day 1 and in the morning on Days 2 through 4. A 50% dosage reduction of dexamethasone is recommended to account for a drug interaction with EMEND [see Clinical Pharmacology (12.3)].]
5-HT3 antagonist | Adults and Pediatric Patients 12 Years and Older | See selected 5-HT3 antagonist prescribing information for the recommended dosage | none | none | none

Table 2: Recommended Dosing for the Prevention of Nausea and Vomiting Associated with MEC
 | Population | Day 1 | Day 2 | Day 3
EMEND capsules [Administer EMEND capsules 1 hour prior to chemotherapy treatment on Days 1, 2, and 3. If no chemotherapy is given on Days 2 and 3, administer EMEND capsules in the morning.] | Adults and Pediatric Patients 12 Years and Older | 125 mg orally | 80 mg orally | 80 mg orally
Dexamethasone | Adults | 12 mg orally | none | none
Dexamethasone | Pediatric Patients 12 Years and Older | If a corticosteroid, such as dexamethasone, is co-administered, administer 50% of the recommended corticosteroid dose on Days 1 through 4 [see Clinical Studies (14.3)]. [Administer dexamethasone 30 minutes prior to chemotherapy treatment on Day 1. A 50% dosage reduction of dexamethasone is recommended to account for a drug interaction with EMEND [see Clinical Pharmacology (12.3)].]
5-HT3 antagonist | Adults and Pediatric Patients 12 Years and Older | See the selected 5-HT3 antagonist prescribing information for recommended dosage | none | none

Pediatric Patients 6 Months to less than 12 Years of Age or Pediatric and Adult Patients Unable to Swallow Capsules

The recommended dose of EMEND for oral suspension to be administered with a 5-HT3 antagonist, with or without a corticosteroid, for the prevention of nausea and vomiting associated with administration of HEC or MEC is specified in Table 3. Dosing of EMEND for oral suspension is based on weight, to a maximum of 125 mg on Day 1 and 80 mg on Days 2 and 3. Dosing in pediatric patients less than 6 kg is not recommended.

Table 3: Recommended Dosing in Pediatric Patients 6 Months to Less than 12 Years of Age or Pediatric and Adult Patients Unable to Swallow Capsules
 | Population | Day 1 | Day 2 | Day 3 | Day 4
EMEND for oral suspension [After preparation, the final concentration of EMEND for oral suspension is 25 mg/mL [see Dosage and Administration (2.3)]. Administer EMEND for oral suspension 1 hour prior to chemotherapy treatment on Days 1, 2, and 3. If no chemotherapy is given on Days 2 and 3, administer EMEND for oral suspension in the morning.] | Pediatric Patients 6 Months to Less than12 Years or Pediatric and Adult Patients Unable to Swallow Capsules | 3 mg/kg orally Maximum dose 125 mg | 2 mg/kg orally Maximum dose 80 mg | 2 mg/kg orally Maximum dose 80 mg | none
Dexamethasone | Adults Unable to Swallow Capsules | See Table 1 or 2 | See Table 1 or 2 | See Table 1 or 2 | See Table 1 or 2
Dexamethasone | Pediatric Patients 6 Months to Less than12 Years or Pediatric Patients Unable to Swallow Capsules | If a corticosteroid, such as dexamethasone, is co-administered, administer 50% of the recommended corticosteroid dose on Days 1 through 4 [see Clinical Studies (14.3)]. [Administer dexamethasone 30 minutes prior to chemotherapy treatment on Day 1. A 50% dosage reduction of dexamethasone is recommended to account for a drug interaction with EMEND [see Clinical Pharmacology (12.3)].]
5-HT3 antagonist | Pediatric Patients 6 Months to Less than12 Years or Pediatric and Adult Patients Unable to Swallow Capsules | See selected 5-HT3 antagonist prescribing information for the recommended dosage | none | none | none

2.2 Preparation Instructions for EMEND for Oral Suspension -- for Healthcare Providers

EMEND for oral suspension should be prepared by a healthcare provider. Once prepared, it may be administered either by a healthcare provider, patient, or caregiver.

Before preparing EMEND:

- Do not open the pouch of EMEND until ready to prepare the medicine.
- Store the pouch at room temperature [between 68°F-77°F (20°C-25°C)].

Table 4: Instructions for Healthcare Providers on How to Prepare EMEND for Oral Suspension
EMEND for oral suspension is packaged as a kit with one 1 mL oral dosing dispenser, one 5 mL oral dosing dispenser, one cap and one mixing cup.
1. Fill the mixing cup with room temperature drinking water.
2. Fill the 5 mL oral dosing dispenser with 4.6 mL of water from the mixing cup. Make sure no air is in the dispenser - if air is present, remove.
3. Discard all the unused water remaining in the mixing cup.
4. Add the 4.6 mL of water from the dispenser back into the mixing cup.
5. Each pouch of EMEND for oral suspension contains 125 mg of aprepitant which is to be suspended in 4.6 mL of water giving a final concentration of 25 mg/mL. Hold the EMEND for oral suspension pouch upright and shake the contents to the bottom before opening the pouch. 6. Pour the entire contents of the pouch into the 4.6 mL of water in the mixing cup and snap the lid shut.
7. Mix the EMEND suspension gently by swirling 20 times; then gently invert the mixing cup 5 times. To prevent foaming, do not shake the mixing cup. The mixture will be cloudy pink to light pink.
8. Check the EMEND mixture for any clumps or foaming: - If any clumps are present, repeat Step 7 until there are no clumps. - If there is any foam, wait for the foam to disappear before going on to Step 9.
9. Fill the dispenser with the prescribed dose shown above in Table 3. - Choose the dispenser based on dose: - Use 1 mL dispenser if dose is 1 mL or less. - Use 5 mL dispenser if dose is more than 1 mL. - Fill the dispenser with the prescribed dose from the cup. - If the dose is less than 1 mL round to the nearest 0.1 mL. - If the dose is more than 1 mL round to the nearest 0.2 mL. - It is common to have medicine leftover in the cup.
Make sure no air is in the dispenser - if air is present, remove. Make sure the dispenser contains the prescribed dose.
10. Place the cap on the dispenser until it clicks. 11. If the dose is not administered immediately after measuring, store filled oral dosing dispenser(s) in the refrigerator [between 36°F-46°F (2°C-8°C)] for up to 72 hours prior to use. When dispensing dose(s) to the patient or caregiver, instruct them to refrigerate the oral dosing dispenser(s) until they are ready to administer the dose. 12. When ready to use, the mixture can be kept at room temperature [between 68°F-77°F (20°C-25°C)] for up to 3 hours.
13. Discard the mixing cup along with any remaining suspension.

2.3 Administration Instructions

EMEND capsules and EMEND for oral suspension can be administered with or without food.

EMEND capsules

- Swallow capsules whole.

EMEND for oral suspension

- The dose will be prepared by the healthcare provider and dispensed to the patient or caregiver in an oral dispenser.
- Keep the dispenser in the refrigerator until administered to the patient. The dose can be stored at room temperature for up to 3 hours before use.
- When ready to use, take the cap off the dispenser, place the dispenser in the patient's mouth along the inner cheek on either the right or left side. Slowly dispense the medicine.
- The dose must be used within 72 hours of preparation.
- Discard any doses remaining after 72 hours.

3 DOSAGE FORMS AND STRENGTHS

EMEND capsules:

- 80 mg: white body and cap with "461" and "80 mg" printed radially in black ink on the body.
- 125 mg: white body and pink cap with "462" and "125 mg" printed radially in black ink on the body.

EMEND for oral suspension:

- 125 mg as a pink to light pink powder in a single-use pouch with one 1 mL oral dosing dispenser, one 5 mL oral dosing dispenser, one cap and mixing cup.

4 CONTRAINDICATIONS

EMEND is contraindicated in patients:

- who are hypersensitive to any component of the product. Hypersensitivity reactions including anaphylactic reactions have been reported [see Adverse Reactions (6.2)].
- taking pimozide. Inhibition of CYP3A4 by aprepitant could result in elevated plasma concentrations of this drug which is a CYP3A4 substrate, potentially causing serious or life-threatening reactions, such as QT prolongation, a known adverse reaction of pimozide [see Warnings and Precautions (5.1)].

5 WARNINGS AND PRECAUTIONS

5.1 Clinically Significant CYP3A4 Drug Interactions

Aprepitant is a substrate, a weak-to-moderate (dose-dependent) inhibitor, and an inducer of CYP3A4.

- Use of EMEND with other drugs that are CYP3A4 substrates, may result in increased plasma concentration of the concomitant drug.
  - Use of pimozide with EMEND is contraindicated due to the risk of significantly increased plasma concentrations of pimozide, potentially resulting in prolongation of the QT interval, a known adverse reaction of pimozide [see Contraindications (4)].
- Use of EMEND with strong or moderate CYP3A4 inhibitors (e.g., ketoconazole, diltiazem) may increase plasma concentrations of aprepitant and result in an increased risk of adverse reactions related to EMEND.
- Use of EMEND with strong CYP3A4 inducers (e.g., rifampin) may result in a reduction in aprepitant plasma concentrations and decreased efficacy of EMEND.

See Table 8 and Table 9 for a listing of potentially significant drug interactions [see Drug Interactions (7.1, 7.2)].

5.2 Decrease in INR with Concomitant Warfarin

Coadministration of EMEND with warfarin, a CYP2C9 substrate, may result in a clinically significant decrease in International Normalized Ratio (INR) of prothrombin time [see Clinical Pharmacology (12.3)]. Monitor the INR in patients on chronic warfarin therapy in the 2-week period, particularly at 7 to 10 days, following initiation of the 3-day regimen of EMEND with each chemotherapy cycle [see Drug Interactions (7.1)].

5.3 Risk of Reduced Efficacy of Hormonal Contraceptives

Upon coadministration with EMEND, the efficacy of hormonal contraceptives may be reduced during administration of and for 28 days following the last dose of EMEND [see Clinical Pharmacology (12.3)]. Advise patients to use effective alternative or back-up methods of contraception during treatment with EMEND and for 1 month following the last dose of EMEND [see Drug Interactions (7.1), Use in Specific Populations (8.3)].

6 ADVERSE REACTIONS

6.1 Clinical Trials Experience

Because clinical trials are conducted under widely varying conditions, adverse reaction rates observed in the clinical trials of a drug cannot be directly compared to rates in the clinical trials of another drug and may not reflect the rates observed in clinical practice.

The overall safety of EMEND was evaluated in approximately 6800 individuals.

Adults

In 2 active-controlled, double-blind clinical trials in patients receiving highly emetogenic chemotherapy (HEC) (Studies 1 and 2), EMEND in combination with ondansetron and dexamethasone (EMEND regimen) was compared to ondansetron and dexamethasone alone (standard therapy) [see Clinical Studies (14.1)].

In 2 active-controlled clinical trials in patients receiving moderately emetogenic chemotherapy (MEC) (Studies 3 and 4), EMEND in combination with ondansetron and dexamethasone (EMEND regimen) was compared to ondansetron and dexamethasone alone (standard therapy) [see Clinical Studies (14.2)]. The most common adverse reaction reported in patients who received MEC in pooled Studies 3 and 4 was dyspepsia (6% versus 4%).

Across these 4 studies there were 1412 patients treated with the EMEND regimen during Cycle 1 of chemotherapy and 1099 of these patients continued into the Multiple-Cycle extension for up to 6 cycles of chemotherapy. The most common adverse reactions reported in patients who received HEC and MEC in pooled Studies 1, 2, 3 and 4 are listed in Table 5.

Table 5: Most Common Adverse Reactions in Patients Receiving HEC and MEC from a Pooled Analysis of HEC and MEC Studies [Reported in ≥ 3% of patients treated with the EMEND regimen and at a greater incidence than standard therapy.]
 | EMEND, ondansetron, and dexamethasone [EMEND regimen] (N=1412) | Ondansetron and dexamethasone [Standard therapy] (N=1396)
fatigue | 13% | 12%
diarrhea | 9% | 8%
asthenia | 7% | 6%
dyspepsia | 7% | 5%
abdominal pain | 6% | 5%
hiccups | 5% | 3%
white blood cell count decreased | 4% | 3%
dehydration | 3% | 2%
alanine aminotransferase increased | 3% | 2%

In a pooled analysis of the HEC and MEC studies, less common adverse reactions reported in patients treated with the EMEND regimen are listed in Table 6.

Table 6: Less Common Adverse Reactions in EMEND-Treated Patients from a Pooled Analysis of HEC and MEC Studies [Reported in > 0.5% of patients treated with the EMEND regimen, at a greater incidence than standard therapy and not previously described in Table 5.]
Infection and Infestations | oral candidiasis, pharyngitis
Blood and the Lymphatic System Disorders | anemia, febrile neutropenia, neutropenia, thrombocytopenia
Metabolism and Nutrition Disorders | decreased appetite, hypokalemia
Psychiatric Disorders | anxiety
Nervous System Disorders | dizziness, dysgeusia, peripheral neuropathy
Cardiac Disorders | palpitations
Vascular Disorders | flushing, hot flush
Respiratory, Thoracic and Mediastinal Disorders | cough, dyspnea, oropharyngeal pain
Gastrointestinal Disorders | dry mouth, eructation, flatulence, gastritis, gastroesophageal reflux disease, nausea, vomiting
Skin and Subcutaneous Tissue Disorders | alopecia, hyperhidrosis, rash
Musculoskeletal and Connective Tissue Disorders | musculoskeletal pain
General Disorders and Administration Site Condition | edema peripheral, malaise
Investigations | aspartate aminotransferase increased, blood alkaline phosphatase increased, blood sodium decreased, blood urea increased, proteinuria, weight decreased

In an additional active-controlled clinical study in 1169 patients receiving EMEND and HEC, the adverse reactions were generally similar to that seen in the other HEC studies with EMEND.

In another CINV study, Stevens-Johnson syndrome was reported as a serious adverse reaction in a patient receiving the EMEND regimen with cancer chemotherapy.

Adverse reactions in the Multiple-Cycle extensions of HEC and MEC studies for up to 6 cycles of chemotherapy were generally similar to that observed in Cycle 1.

Pediatric Patients 6 Months to 17 Years of Age

In a pooled analysis of 2 active-controlled clinical trials in pediatric patients aged 6 months to 17 years who received highly or moderately emetogenic cancer chemotherapy (Study 5 and a safety study, Study 6), EMEND in combination with ondansetron with or without dexamethasone (EMEND regimen) was compared to ondansetron with or without dexamethasone (control regimen).

There were 184 patients treated with the EMEND regimen during Cycle 1 and 215 patients received open-label EMEND for up to 9 additional cycles of chemotherapy.

In Cycle 1, the most common adverse reactions reported in pediatric patients treated with the EMEND regimen in pooled Studies 5 and 6 are listed in Table 7.

Table 7: Most Common Adverse Reactions in EMEND-Treated Pediatric Patients in HEC and MEC Pooled Studies 5 and 6 [Reported in ≥3% of patients treated with the EMEND regimen and at a greater incidence than control regimen.]
 | EMEND and ondansetron [EMEND regimen] (N=184) | Ondansetron [Control regimen] (N=168)
neutropenia | 13% | 11%
headache | 9% | 5%
diarrhea | 6% | 5%
decreased appetite | 5% | 4%
cough | 5% | 3%
fatigue | 5% | 2%
hemoglobin decreased | 5% | 4%
dizziness | 5% | 1%
hiccups | 4% | 1%

Forty-nine patients were treated with ifosfamide chemotherapy in each arm. Two of the patients treated with ifosfamide in the aprepitant arm developed behavioral changes (agitation = 1; abnormal behavior = 1), whereas no patient treated with ifosfamide in the control arm developed behavioral changes. Aprepitant has the potential for increasing ifosfamide-mediated neurotoxicity through induction of CYP3A4 [see Drug Interactions (7.1) and Clinical Pharmacology (12.3)].

Non-CINV Studies

Serious adverse reactions reported in adult patients receiving a non-recommended dosage of EMEND in non-CINV studies include single cases of each of the following: angioedema and urticaria, constipation, and sub-ileus. EMEND is only approved in the CINV population.

6.2 Postmarketing Experience

The following adverse reactions have been identified during post-approval use of EMEND. Because these reactions are reported voluntarily from a population of uncertain size, it is not always possible to reliably estimate their frequency or establish a causal relationship to drug exposure.

Skin and subcutaneous tissue disorders: pruritus, rash, urticaria, Stevens-Johnson syndrome/toxic epidermal necrolysis.

Immune system disorders: hypersensitivity reactions including anaphylactic reactions [see Contraindications (4)].

Nervous system disorders: ifosfamide-induced neurotoxicity reported after EMEND and ifosfamide coadministration.

7 DRUG INTERACTIONS

7.1 Effect of Aprepitant on the Pharmacokinetics of Other Drugs

Aprepitant is a substrate, a weak-to-moderate (dose-dependent) inhibitor, and an inducer of CYP3A4. Aprepitant is also an inducer of CYP2C9 [see Clinical Pharmacology (12.3)].

Aprepitant acts as a moderate inhibitor of CYP3A4 when administered as a 3-day regimen (125-mg/80-mg/80-mg) and can increase plasma concentrations of concomitant drugs that are substrates for CYP3A4. Some substrates of CYP3A4 are contraindicated with EMEND [see Contraindications (4)]. Dosage adjustment of some CYP3A4 and CYP2C9 substrates may be warranted, as shown in Table 8.

Table 8: Effects of Aprepitant on the Pharmacokinetics of Other Drugs
CYP3A4 Substrates
Pimozide
Clinical Impact | Increased pimozide exposure.
Intervention | EMEND is contraindicated [see Contraindications (4)].
Benzodiazepines
Clinical Impact | Increased exposure to midazolam or other benzodiazepines metabolized via CYP3A4 (alprazolam, triazolam) may increase the risk of adverse reactions [see Clinical Pharmacology (12.3)].
Intervention | - Monitor for benzodiazepine-related adverse reactions. - Depending on the clinical situation (e.g., elderly patients) and degree of monitoring available, reduce the dose of intravenous midazolam
Dexamethasone
Clinical Impact | Increased dexamethasone exposure [see Clinical Pharmacology (12.3)].
Intervention | Reduce the dose of oral dexamethasone by approximately 50% [see Dosage and Administration (2.1)].
Methylprednisolone
Clinical Impact | Increased methylprednisolone exposure [see Clinical Pharmacology (12.3)].
Intervention | - Reduce the dose of intravenous methylprednisolone by approximately 25% - Reduce the dose of oral methylprednisolone by approximately 50%
Chemotherapeutic agents that are metabolized by CYP3A4
Clinical Impact | Increased exposure of the chemotherapeutic agent may increase the risk of adverse reactions [see Clinical Pharmacology (12.3)].
Intervention | Vinblastine, vincristine, or ifosfamide or other chemotherapeutic agents; - Monitor for chemotherapeutic-related adverse reactions.; Etoposide, vinorelbine, paclitaxel, and docetaxel; - No dosage adjustment needed.
Hormonal Contraceptives
Clinical Impact | Decreased hormonal exposure during administration of and for 28 days after administration of the last dose of EMEND [see Warnings and Precautions (5.3), Use in Specific Populations (8.3), Clinical Pharmacology (12.3)].
Intervention | Effective alternative or back-up methods of contraception (such as condoms and spermicides) should be used during treatment with EMEND and for 1 month following the last dose of EMEND.
Examples | birth control pills, skin patches, implants, and certain IUDs
CYP2C9 Substrates
Warfarin
Clinical Impact | Decreased warfarin exposure and decreased prothrombin time (INR) [see Warnings and Precautions (5.2), Clinical Pharmacology (12.3)].
Intervention | In patients on chronic warfarin therapy, monitor the prothrombin time (INR) in the 2-week period, particularly at 7 to 10 days, following initiation of the 3-day EMEND regimen with each chemotherapy cycle.
Other
5-HT3 Antagonists
Clinical Impact | No change in the exposure of the 5-HT3 antagonist [see Clinical Pharmacology (12.3)].
Intervention | No dosage adjustment needed
Examples | ondansetron, granisetron, dolasetron

7.2 Effect of Other Drugs on the Pharmacokinetics of Aprepitant

Aprepitant is a CYP3A4 substrate [see Clinical Pharmacology (12.3)]. Co-administration of EMEND with drugs that are inhibitors or inducers of CYP3A4 may result in increased or decreased plasma concentrations of aprepitant, respectively, as shown in Table 9.

Table 9: Effects of Other Drugs on Pharmacokinetics of Aprepitant
Moderate to Strong CYP3A4 Inhibitors
Clinical Impact | Significantly increased exposure of aprepitant may increase the risk of adverse reactions associated with EMEND [see Adverse Reactions (6.1) and Clinical Pharmacology (12.3)].
Intervention | Avoid concomitant use of EMEND.
Examples | Moderate inhibitor: diltiazem Strong inhibitors: ketoconazole, itraconazole, nefazodone, troleandomycin, clarithromycin, ritonavir, nelfinavir
Strong CYP3A4 Inducers
Clinical Impact | Substantially decreased exposure of aprepitant in patients chronically taking a strong CYP3A4 inducer may decrease the efficacy of EMEND [see Clinical Pharmacology (12.3)].
Intervention | Avoid concomitant use of EMEND.
Examples | rifampin, carbamazepine, phenytoin

8 USE IN SPECIFIC POPULATIONS

8.1 Pregnancy

Risk Summary

There are insufficient data on use of EMEND in pregnant women to inform a drug associated risk. In animal reproduction studies, no adverse developmental effects were observed in rats or rabbits exposed during the period of organogenesis to systemic drug levels (AUC) approximately 1.5 times the adult human exposure at the 125-mg/80-mg/80-mg EMEND regimen [see Data].

The estimated background risk of major birth defects and miscarriage for the indicated populations is unknown. In the U.S. general population, the estimated background risk of major birth defects and miscarriage in clinically recognized pregnancies is 2 to 4% and 15 to 20%, respectively.

Data

Animal Data

In embryofetal development studies in rats and rabbits, aprepitant was administered during the period of organogenesis at oral doses up to 1000 mg/kg twice daily in rats and up to the maximum tolerated dose of 25 mg/kg/day in rabbits. No embryofetal lethality or malformations were observed at any dose level in either species. The exposures (AUC) in pregnant rats at 1000 mg/kg twice daily and in pregnant rabbits at 125 mg/kg/day were approximately 1.5 times the adult exposure at the 125-mg/80-mg/80-mg EMEND regimen. Aprepitant crosses the placenta in rats and rabbits.

8.2 Lactation

Risk Summary

Lactation studies have not been conducted to assess the presence of aprepitant in human milk, the effects on the breastfed infant, or the effects on milk production. Aprepitant is present in rat milk. The developmental and health benefits of breastfeeding should be considered along with the mother's clinical need for EMEND and any potential adverse effects on the breastfed infant from EMEND or from the underlying maternal condition.

8.3 Females and Males of Reproductive Potential

Contraception

Upon administration of EMEND, the efficacy of hormonal contraceptives may be reduced. Advise females of reproductive potential using hormonal contraceptives to use an effective alternative or back-up non-hormonal contraceptive (such as condoms and spermicides) during treatment with EMEND and for 1 month following the last dose [see Drug Interactions (7.1), Clinical Pharmacology (12.3)].

8.4 Pediatric Use

The safety and effectiveness of EMEND for oral suspension have been established in pediatric patients 6 months of age and older and EMEND capsules in pediatric patients 12 years of age and older for the prevention of acute and delayed nausea and vomiting associated with initial and repeat courses of HEC, including high-dose cisplatin, and MEC. Use of EMEND in these age groups is supported by evidence from 302 pediatric patients in a randomized, double-blind, active comparator controlled clinical study (n = 207 patients aged 6 months to less than 12 years, n = 95 patients aged 12 through 17 years). EMEND was studied in combination with ondansetron with or without dexamethasone (at the discretion of the physician) [see Clinical Studies (14.3)]. Adverse reactions were similar to those reported in adult patients [see Adverse Reactions (6.1)].

The safety and effectiveness of EMEND for the prevention of nausea and vomiting associated with HEC or MEC have not been established in patients less than 6 months.

Juvenile Animal Study

A study was conducted in young rats to evaluate the effects of aprepitant on growth and on neurobehavioral and sexual development. Rats were treated at oral doses up to the maximum feasible dose of 1000 mg/kg twice daily (providing exposure in male rats lower than the exposure at the recommended pediatric human dose and exposure in female rats equivalent to the pediatric human exposure) from the early postnatal period (Postnatal Day 10) through Postnatal Day 58. Slight changes in the onset of sexual maturation were observed in female and male rats; however, there were no effects on mating, fertility, embryonic-fetal survival, or histomorphology of the reproductive organs. There were no effects in neurobehavioral tests of sensory function, motor function, and learning and memory.

8.5 Geriatric Use

Of the 544 adult cancer patients treated with EMEND in CINV clinical studies, 31% were aged 65 and over, while 5% were aged 75 and over. Other reported clinical experience with EMEND has not identified differences in responses between elderly and younger patients. In general, use caution when dosing elderly patients as they have a greater frequency of decreased hepatic, renal or cardiac function and concomitant disease or other drug therapy [see Clinical Pharmacology (12.3)].

8.6 Patients with Renal Impairment

The pharmacokinetics of aprepitant in patients with severe renal impairment and those with end stage renal disease (ESRD) requiring hemodialysis were similar to those of healthy subjects with normal renal function. No dosage adjustment is necessary for patients with any degree of renal impairment or for patients with ESRD undergoing hemodialysis.

8.7 Patients with Hepatic Impairment

The pharmacokinetics of aprepitant in patients with mild and moderate hepatic impairment were similar to those of healthy subjects with normal hepatic function. No dosage adjustment is necessary for patients with mild to moderate hepatic impairment (Child-Pugh score 5 to 9). There are no clinical or pharmacokinetic data in patients with severe hepatic impairment (Child-Pugh score greater than 9). Therefore, additional monitoring for adverse reactions in these patients may be warranted when EMEND is administered [see Clinical Pharmacology (12.3)].

10 OVERDOSAGE

No specific information is available on the treatment of overdosage.

Drowsiness and headache were reported in one patient who ingested 1440 mg of EMEND (approximately 11 times the maximum recommended single dose).

In the event of overdose, EMEND should be discontinued and general supportive treatment and monitoring should be provided. Because of the antiemetic activity of EMEND, drug-induced emesis may not be effective in cases of EMEND overdosage.

Aprepitant is not removed by hemodialysis.

11 DESCRIPTION

EMEND capsules contain the active ingredient, aprepitant. Aprepitant is a substance P/neurokinin 1 (NK1) receptor antagonist, an antiemetic agent, chemically described as 5-[[(2R,3S)-2-[(1R)-1-[3,5-bis(trifluoromethyl)phenyl]ethoxy]-3-(4-fluorophenyl)-4-morpholinyl]methyl]-1,2-dihydro-3H-1,2,4-triazol-3-one.

Its empirical formula is C23H21F7N4O3, and its structural formula is:

Aprepitant is a white to off-white crystalline solid, with a molecular weight of 534.43. It is practically insoluble in water. Aprepitant is sparingly soluble in ethanol and isopropyl acetate and slightly soluble in acetonitrile.

Each capsule of EMEND for oral administration contains either 80 mg or 125 mg of aprepitant and the following inactive ingredients: sucrose, microcrystalline cellulose, hydroxypropyl cellulose and sodium lauryl sulfate. The capsule shell excipients are gelatin, titanium dioxide, and may contain sodium lauryl sulfate and silicon dioxide. The 125-mg capsule also contains red ferric oxide and yellow ferric oxide.

Each pouch of EMEND for oral suspension 125 mg contains 125 mg of aprepitant and the following inactive ingredients: sucrose, lactose, hydroxypropyl cellulose, sodium lauryl sulfate, red iron oxide, and sodium stearyl fumarate.

12 CLINICAL PHARMACOLOGY

12.1 Mechanism of Action

Aprepitant is a selective high-affinity antagonist of human substance P/neurokinin 1 (NK1) receptors. Aprepitant has little or no affinity for serotonin (5-HT3), dopamine, and corticosteroid receptors, the targets of existing therapies for chemotherapy-induced nausea and vomiting (CINV).

Aprepitant has been shown in animal models to inhibit emesis induced by cytotoxic chemotherapeutic agents, such as cisplatin, via central actions. Animal and human Positron Emission Tomography (PET) studies with aprepitant have shown that it crosses the blood brain barrier and occupies brain NK1 receptors. Animal and human studies show that aprepitant augments the antiemetic activity of the 5-HT3-receptor antagonist ondansetron and the corticosteroid dexamethasone and inhibits both the acute and delayed phases of cisplatin-induced emesis.

12.2 Pharmacodynamics

NK1 Receptor Occupancy

In two single-blind, multiple-dose, randomized, and placebo-controlled studies, healthy young men received oral EMEND doses of 10 mg (N=2), 30 mg (N=3), 100 mg (N=3) or 300 mg (N=5) once daily (0.08, 0.24, 0.8, and 2.4 times the maximum recommended single dose, respectively) for 14 days with 2 or 3 subjects on placebo. Both plasma aprepitant concentration and NK1 receptor occupancy in the corpus striatum by positron emission tomography were evaluated, at predose and 24 hours after the last dose. At aprepitant plasma concentrations of approximately 10 ng/mL and 100 ng/mL, the NK1 receptor occupancies were approximately 50% and 90%, respectively. The oral EMEND regimen produced mean trough plasma aprepitant concentrations greater than 500 ng/mL in adults, which would be expected to, based on the fitted curve with the Hill equation, result in greater than 95% brain NK1 receptor occupancy. However, the receptor occupancy has not been determined. In addition, the relationship between NK1 receptor occupancy and the clinical efficacy of EMEND has not been established.

Cardiac Electrophysiology

In a randomized, double-blind, positive-controlled, thorough QTc study, a single 200-mg dose of fosaprepitant had no effect on the QTc interval. Maximum aprepitant concentrations after a single 200-mg dose of fosaprepitant were 4-fold higher than that achieved with oral EMEND 125 mg. QT prolongation with the recommended oral EMEND dosing regimens is not expected.

12.3 Pharmacokinetics

Absorption

Following oral administration of a single 125-mg dose of EMEND on Day 1 and 80 mg once daily on Days 2 and 3, the AUC0-24hr was approximately 19.6 mcg∙hr/mL and 21.2 mcg∙hr/mL on Day 1 and Day 3, respectively. The Cmax of 1.6 mcg/mL and 1.4 mcg/mL were reached in approximately 4 hours (Tmax) on Day 1 and Day 3, respectively. At the dose range of 80 to 125 mg, the mean absolute oral bioavailability of EMEND is approximately 60 to 65%. Oral administration of the capsule with a standard high-fat breakfast had no clinically meaningful effect on the bioavailability of aprepitant.

The pharmacokinetics of aprepitant were non-linear across the clinical dose range. In healthy young adults, the increase in AUC0-∞ was 26% greater than dose proportional between 80-mg and 125-mg single doses administered in the fed state.

Distribution

Aprepitant is greater than 95% bound to plasma proteins. The mean apparent volume of distribution at steady state (Vdss) was approximately 70 L in humans.

Aprepitant crosses the blood brain barrier in humans [see Clinical Pharmacology (12.1)].

Elimination

Metabolism

Aprepitant undergoes extensive metabolism. In vitro studies using human liver microsomes indicate that aprepitant is metabolized primarily by CYP3A4 with minor metabolism by CYP1A2 and CYP2C19. Metabolism is largely via oxidation at the morpholine ring and its side chains. No metabolism by CYP2D6, CYP2C9, or CYP2E1 was detected. In healthy young adults, aprepitant accounts for approximately 24% of the radioactivity in plasma over 72 hours following a single oral 300-mg dose of [^14C]-aprepitant (2.4 times the maximum EMEND recommended dose), indicating a substantial presence of metabolites in the plasma. Seven metabolites of aprepitant, which are only weakly active, have been identified in human plasma.

Excretion

Following administration of a single intravenous 100-mg dose of [^14C]-aprepitant prodrug to healthy subjects, 57% of the radioactivity was recovered in urine and 45% in feces. A study was not conducted with radiolabeled capsule formulation. The results after oral administration may differ.

Aprepitant is eliminated primarily by metabolism; aprepitant is not renally excreted. The apparent plasma clearance of aprepitant ranged from approximately 62 to 90 mL/min. The apparent terminal half-life ranged from approximately 9 to 13 hours.

Specific Populations

Geriatric Patients

Following oral administration of a single 125-mg dose of EMEND on Day 1 and 80 mg once daily on Days 2 through 5 (2 additional days of dosing compared to the recommended duration), the AUC0-24hr of aprepitant was 21% higher on Day 1 and 36% higher on Day 5 in elderly (65 years and older) relative to younger adults. The Cmax was 10% higher on Day 1 and 24% higher on Day 5 in elderly relative to younger adults. These differences are not considered clinically meaningful [see Use in Specific Populations (8.5)].

Pediatric Patients

As part of a 3-day regimen, dosing of aprepitant capsules (125-mg/80-mg/80-mg) in 18 pediatric patients (aged 12 through 17 years) achieved a mean AUC0-24hr of 17 mcg∙hr/mL on Day 1 with mean peak plasma concentration (Cmax) at 1.3 mcg/mL occurring at approximately 4 hours. The mean concentrations at the end of Day 2 (N=8) and Day 3 (N=16) were both at 0.6 mcg/mL

As part of a 3-day regimen, weight-based dosing of aprepitant powder for oral suspension (3-mg/kg;2-mg/kg;2-mg/kg) in 18 pediatric patients aged 6 months to less than 12 years achieved a mean AUC0-24hr of 20.9 mcg∙hr/mL on Day 1 with mean peak plasma concentration (Cmax) at 1.8 mcg/mL (N=19), occurring at approximately 6 hours. The mean concentrations at the end of Day 2 (N=18) and Day 3 (N=19) were 0.4 mcg/mL and 0.5 mcg/mL, respectively [see Dosage and Administration (2.1)].

A population pharmacokinetic analysis of aprepitant in pediatric patients (aged 6 months through 17 years) suggests that sex and race have no clinically meaningful effect on the pharmacokinetics of aprepitant.

Male and Female Patients

Following oral administration of a single dose of aprepitant ranging from 40 mg to 375 mg (3 times the maximum EMEND recommended dose), the AUC0-24hr and Cmax are 9% and 17% higher in females as compared with males. The half-life of aprepitant is approximately 25% lower in females as compared with males and Tmax occurs at approximately the same time. These differences are not considered clinically meaningful.

Racial or Ethnic Groups

Following oral administration of a single dose of aprepitant ranging from 40 mg to 375 mg (3 times the maximum EMEND recommended dose), the AUC0-24hr and Cmax are approximately 27% and 19% higher in Hispanics as compared with Caucasians. The AUC0-24hr and Cmax were 74% and 47% higher in Asians as compared to Caucasians. There was no difference in AUC0-24hr or Cmax between Caucasians and Blacks. These differences are not considered clinically meaningful.

Patients with Renal Impairment

A single 240-mg dose of aprepitant (approximately 1.9 times the maximum EMEND recommended dose) was administered to patients with severe renal impairment (creatinine clearance less than 30 mL/min/1.73 m^2 as measured by 24-hour urinary creatinine clearance) and to patients with end stage renal disease (ESRD) requiring hemodialysis.

In patients with severe renal impairment, the AUC0-∞ of total aprepitant (unbound and protein bound) decreased by 21% and Cmax decreased by 32%, relative to healthy subjects (creatinine clearance greater than 80 mL/min estimated by Cockcroft-Gault method). In patients with ESRD undergoing hemodialysis, the AUC0-∞ of total aprepitant decreased by 42% and Cmax decreased by 32%. Due to modest decreases in protein binding of aprepitant in patients with renal disease, the AUC of pharmacologically active unbound drug was not significantly affected in patients with renal impairment compared with healthy subjects. Hemodialysis conducted 4 or 48 hours after dosing had no significant effect on the pharmacokinetics of aprepitant; less than 0.2% of the dose was recovered in the dialysate [see Use in Specific Populations (8.6)].

Patients with Hepatic Impairment

Following administration of a single 125-mg dose of EMEND on Day 1 and 80 mg once daily on Days 2 and 3 to patients with mild hepatic impairment (Child-Pugh score 5 to 6), the AUC0-24hr of aprepitant was 11% lower on Day 1 and 36% lower on Day 3, as compared with healthy subjects given the same regimen. In patients with moderate hepatic impairment (Child-Pugh score 7 to 9), the AUC0-24hr of aprepitant was 10% higher on Day 1 and 18% higher on Day 3, as compared with healthy subjects given the same regimen. These differences in AUC0-24hr are not considered clinically meaningful. There are no clinical or pharmacokinetic data in patients with severe hepatic impairment (Child-Pugh score greater than 9) [see Use in Specific Populations (8.7)].

Body Mass Index (BMI)

For every 5 kg/m^2 increase in BMI, AUC0-24hr and Cmax of aprepitant decrease by 9% and 10%. BMI of subjects in the analysis ranged from 18 kg/m^2 to 36 kg/m^2. This change is not considered clinically meaningful.

Drug Interactions Studies

Aprepitant is a substrate, a moderate (dose-dependent) inhibitor, and an inducer of CYP3A4. Aprepitant is also an inducer of CYP2C9. Aprepitant is unlikely to interact with drugs that are substrates for the P-glycoprotein transporter.

Effects of Aprepitant on the Pharmacokinetics of Other Drugs

CYP3A4 substrates (i.e., midazolam): Interactions between EMEND and coadministered midazolam are listed in Table 10 (increase is indicated as "↑", decrease as "↓", no change as "↔").

Table 10: Pharmacokinetic Interaction Data for EMEND and Coadministered Midazolam
Dosage of EMEND | Dosage of Midazolam | Observed Drug Interactions
EMEND 125 mg on Day 1 and 80 mg on Days 2 to 5 | oral 2 mg single dose on Days 1 and 5 | midazolam AUC ↑ 2.3-fold on Day 1 and ↑ 3.3-fold on Day 5 [see Drug Interactions (7.1)]
EMEND 125 mg on Day 1 and 80 mg on Days 2 and 3 | intravenous 2 mg prior to 3-day regimen of EMEND and on Days 4, 8 and 15 | midazolam AUC ↑ 25% on Day 4, AUC ↓ 19% on Day 8 and AUC ↓ 4% on Day 15
EMEND 125 mg on Day 1 | intravenous 2 mg given 1 hour after EMEND | midazolam AUC ↑ 1.5-fold

A difference of less than 2-fold increase of midazolam AUC is not considered clinically important.

Corticosteroids:

Dexamethasone: EMEND, when given as a regimen of 125 mg on Day 1 and 80 mg/day on Days 2 through 5, coadministered with 20-mg dexamethasone on Day 1 and 8-mg dexamethasone on Days 2 through 5, increased the AUC of dexamethasone by 2.2-fold on Days 1 and 5 [see Dosage and Administration (2.1)].

Methylprednisolone: EMEND, when given as a regimen of 125 mg on Day 1 and 80 mg/day on Days 2 and 3, coadministered with 125 mg methylprednisolone IV on Day 1 and 40 mg methylprednisolone orally on Days 2 and 3, increased the AUC of methylprednisolone by 1.34-fold on Day 1 and by 2.5-fold on Day 3.

Chemotherapeutic agents:

Docetaxel: In a pharmacokinetic study, EMEND (125-mg/80-mg/80-mg regimen) did not influence the pharmacokinetics of docetaxel.

Vinorelbine: In a pharmacokinetic study, EMEND (125-mg/80-mg/80-mg regimen) did not influence the pharmacokinetics of vinorelbine to a clinically significant degree.

CYP2C9 substrates (Warfarin, Tolbutamide):

Warfarin: A single 125-mg dose of EMEND was administered on Day 1 and 80 mg/day on Days 2 and 3 to healthy subjects who were stabilized on chronic warfarin therapy. Although there was no effect of EMEND on the plasma AUC of R(+) or S(-) warfarin determined on Day 3, there was a 34% decrease in S(-) warfarin trough concentration accompanied by a 14% decrease in the prothrombin time (reported as International Normalized Ratio or INR) 5 days after completion of dosing with EMEND [see Drug Interactions (7.1)].

Tolbutamide: EMEND, when given as 125 mg on Day 1 and 80 mg/day on Days 2 and 3, decreased the AUC of tolbutamide by 23% on Day 4, 28% on Day 8, and 15% on Day 15, when a single dose of tolbutamide 500 mg was administered prior to the administration of the 3-day regimen of EMEND and on Days 4, 8, and 15. This effect was not considered clinically important.

Other Drugs

Oral contraceptives: When EMEND was administered as a 3-day regimen (125-mg/80-mg/80-mg) with ondansetron and dexamethasone, and coadministered with an oral contraceptive containing ethinyl estradiol and norethindrone, the trough concentrations of both ethinyl estradiol and norethindrone were reduced by as much as 64% for 3 weeks post-treatment.

P-glycoprotein substrates: EMEND is unlikely to interact with drugs that are substrates for the P-glycoprotein transporter, as demonstrated by the lack of interaction of EMEND with digoxin in a clinical drug interaction study.

5-HT3 antagonists: In clinical drug interaction studies, aprepitant did not have clinically important effects on the pharmacokinetics of ondansetron, granisetron, or hydrodolasetron (the active metabolite of dolasetron).

Effect of Other Drugs on the Pharmacokinetics of Aprepitant

Ketoconazole: When a single 125-mg dose of EMEND was administered on Day 5 of a 10-day regimen of 400 mg/day of ketoconazole, a strong CYP3A4 inhibitor, the AUC of aprepitant increased approximately 5-fold and the mean terminal half-life of aprepitant increased approximately 3-fold [see Drug Interactions (7.2)].

Rifampin: When a single 375-mg dose of aprepitant (3 times the maximum EMEND recommended dose) was administered on Day 9 of a 14-day regimen of 600 mg/day of rifampin, a strong CYP3A4 inducer, the AUC of aprepitant decreased approximately 11-fold and the mean terminal half-life decreased approximately 3-fold [see Drug Interactions (7.2)].

Diltiazem: In patients with mild to moderate hypertension, administration of aprepitant once daily, as a tablet formulation comparable to 230 mg of the capsule formulation (approximately 1.8 times the EMEND recommended dose), with diltiazem 120 mg 3 times daily for 5 days, resulted in a 2-fold increase of aprepitant AUC and a simultaneous 1.7-fold increase of diltiazem AUC. These pharmacokinetic effects did not result in clinically meaningful changes in ECG, heart rate or blood pressure beyond those changes induced by diltiazem alone [see Drug Interactions (7.2)].

Paroxetine: Coadministration of once daily doses of aprepitant, as a tablet formulation comparable to 85 mg or 170 mg of the capsule formulation (approximately 0.7 and 1.4 times the maximum EMEND recommended dose), with paroxetine 20 mg once daily, resulted in a decrease in AUC by approximately 25% and Cmax by approximately 20% of both aprepitant and paroxetine. This effect was not considered clinically important.

13 NONCLINICAL TOXICOLOGY

13.1 Carcinogenesis, Mutagenesis, Impairment of Fertility

Carcinogenesis

Carcinogenicity studies were conducted in Sprague-Dawley rats and in CD-1 mice for 2 years. In the rat carcinogenicity studies, animals were treated with oral doses ranging from 0.05 to 1000 mg/kg twice daily. The highest dose produced a systemic exposure to aprepitant (AUC) of 0.7 to 1.6 times the adult human exposure at the 125-mg/80-mg/80-mg EMEND regimen. Treatment with aprepitant at doses of 5 to 1000 mg/kg twice daily caused an increase in the incidences of thyroid follicular cell adenomas and carcinomas in male rats. In female rats, it produced hepatocellular adenomas at 5 to 1000 mg/kg twice daily and hepatocellular carcinomas and thyroid follicular cell adenomas at 125 to 1000 mg/kg twice daily. In the mouse carcinogenicity studies, the animals were treated with oral doses ranging from 2.5 to 2000 mg/kg/day. The highest dose produced a systemic exposure of about 2.8 to 3.6 times the adult human exposure at the 125-mg/80-mg/80-mg EMEND regimen. Treatment with aprepitant produced skin fibrosarcomas at 125 and 500 mg/kg/day doses in male mice.

Mutagenesis

Aprepitant was not genotoxic in the Ames test, the human lymphoblastoid cell (TK6) mutagenesis test, the rat hepatocyte DNA strand break test, the Chinese hamster ovary (CHO) cell chromosome aberration test and the mouse micronucleus test.

Impairment of Fertility

Aprepitant did not affect the fertility or general reproductive performance of male or female rats at doses up to the maximum feasible dose of 1000 mg/kg twice daily (providing exposure in male rats lower than the exposure at the recommended adult human dose and exposure in female rats at about 1.6 times the adult human exposure at the 125-mg/80-mg/80-mg EMEND regimen).

14 CLINICAL STUDIES

14.1 Prevention of Nausea and Vomiting Associated with HEC in Adults

Oral administration of EMEND in combination with ondansetron and dexamethasone (EMEND regimen) has been shown to prevent acute and delayed nausea and vomiting associated with HEC including high-dose cisplatin, and nausea and vomiting associated with MEC.

In Studies 1 and 2, both multicenter, randomized, parallel, double-blind, controlled clinical studies in adults, EMEND in combination with ondansetron and dexamethasone was compared with standard therapy (ondansetron and dexamethasone alone) in patients receiving a chemotherapy regimen that included cisplatin greater than 50 mg/m^2 (mean cisplatin dose = 80.2 mg/m^2). See Table 11.

In these studies, 95% of the patients in the EMEND group received a concomitant chemotherapeutic agent in addition to protocol-mandated cisplatin. The most common chemotherapeutic agents and the number of EMEND patients exposed follows: etoposide (106), fluorouracil (100), gemcitabine (89), vinorelbine (82), paclitaxel (52), cyclophosphamide (50), doxorubicin (38), docetaxel (11).

Of the 550 patients who were randomized to receive the EMEND regimen, 42% were women, 58% men, 59% White, 3% Asian, 5% Black, 12% Hispanic American, and 21% Multi-Racial. The EMEND-treated patients in these clinical studies ranged from 14 to 84 years of age, with a mean age of 56 years. A total of 170 patients were 65 years or older, with 29 patients being 75 years or older.

Table 11: HEC Treatment Regimens – Studies 1 and 2 [EMEND placebo and dexamethasone placebo were used to maintain blinding.]
 | Day 1 | Day 2 | Day 3 | Day 4
CINV EMEND Regimen
Oral EMEND [EMEND was administered 1 hour prior to chemotherapy treatment on Day 1 and in the morning on Days 2 and 3.] | 125 mg | 80 mg | 80 mg | none
Oral Dexamethasone [Dexamethasone was administered 30 minutes prior to chemotherapy treatment on Day 1 and in the morning on Days 2 through 4. The 12 mg dose of dexamethasone on Day 1 reflects a dosage adjustment to account for a drug interaction with the EMEND regimen [see Clinical Pharmacology (12.3)].] | 12 mg | 8 mg | 8 mg | 8 mg
Ondansetron | 5-HT3 antagonist [Ondansetron 32 mg intravenous was used in the clinical trials of EMEND. Although this dose was used in clinical trials, this is no longer the currently recommended dose. Refer to the ondansetron prescribing information for the current recommended dose.] | none | none | none
CINV Standard Therapy
Oral Dexamethasone | 20 mg | 8 mg twice daily | 8 mg twice daily | 8 mg twice daily
Ondansetron | 5-HT3 antagonist | none | none | none

The antiemetic activity of EMEND was evaluated during the acute phase (0 to 24 hours post-cisplatin treatment), the delayed phase (25 to 120 hours post-cisplatin treatment) and overall (0 to 120 hours post-cisplatin treatment) in Cycle 1. Efficacy was based on evaluation of the following endpoints in which emetic episodes included vomiting, retching, or dry heaves:

Primary endpoint:

- complete response (defined as no emetic episodes and no use of rescue therapy as recorded in patient diaries)

Other prespecified endpoints:

- complete protection (defined as no emetic episodes, no use of rescue therapy, and a maximum nausea visual analogue scale [VAS] score less than 25 mm on a 0 to 100 mm scale)
- no emesis (defined as no emetic episodes regardless of use of rescue therapy)
- no nausea (maximum VAS less than 5 mm on a 0 to 100 mm scale)
- no significant nausea (maximum VAS less than 25 mm on a 0 to 100 mm scale)

A summary of the key study results from each individual study analysis is shown in Table 12. In both studies, a statistically significantly higher proportion of patients receiving the EMEND regimen in Cycle 1 had a complete response in the overall phase (primary endpoint), compared with patients receiving standard therapy. A statistically significant difference in complete response in favor of the EMEND regimen was also observed when the acute phase and the delayed phase were analyzed separately.

Table 12: Percent of Patients Receiving HEC Responding by Treatment Group and Phase — Cycle 1
 | Study 1 |  |  | Study 2
ENDPOINTS | EMEND Regimen (N=260) [N: Number of patients (older than 18 years of age) who received cisplatin, study drug, and had at least one post-treatment efficacy evaluation.] % | Standard Therapy (N=261) % | p-Value | EMEND Regimen (N=261) % | Standard Therapy (N=263) % | p-Value
PRIMARY ENDPOINT
Complete Response
Overall [Overall: 0 to 120 hours post-cisplatin treatment.] | 73 | 52 | <0.001 | 63 | 43 | <0.001
OTHER PRESPECIFIED ENDPOINTS
Complete Response
Acute phase [Acute phase: 0 to 24 hours post-cisplatin treatment.] | 89 | 78 | <0.001 | 83 | 68 | <0.001
Delayed phase [Delayed phase: 25 to 120 hours post-cisplatin treatment.] | 75 | 56 | <0.001 | 68 | 47 | <0.001
Complete Protection
Overall | 63 | 49 | 0.001 | 56 | 41 | <0.001
Acute phase | 85 | 75 | NS [Not statistically significant when adjusted for multiple comparisons.] | 80 | 65 | <0.001
Delayed phase | 66 | 52 | <0.001 | 61 | 44 | <0.001
No Emesis
Overall | 78 | 55 | <0.001 | 66 | 44 | <0.001
Acute phase | 90 | 79 | 0.001 | 84 | 69 | <0.001
Delayed phase | 81 | 59 | <0.001 | 72 | 48 | <0.001
No Nausea
Overall | 48 | 44 | NS [Not statistically significant.] | 49 | 39 | NS
Delayed phase | 51 | 48 | NS | 53 | 40 | NS
No Significant Nausea
Overall | 73 | 66 | NS | 71 | 64 | NS
Delayed phase | 75 | 69 | NS | 73 | 65 | NS
Visual analogue scale (VAS) score range: 0 mm=no nausea; 100 mm=nausea as bad as it could be.

In both studies, the estimated time to first emesis after initiation of cisplatin treatment was longer with the EMEND regimen, and the incidence of first emesis was reduced in the EMEND regimen group compared with standard therapy group as depicted in the Kaplan-Meier curves in Figure 1.

Figure 1: Percent of Patients Receiving HEC Who Remain Emesis Free Over Time — Cycle 1

p-Value <0.001 based on a log rank test for Study 1 and Study 2; nominal p-values not adjusted for multiplicity.

Additional Patient-Reported Outcomes: The impact of nausea and vomiting on patients' daily lives was assessed in Cycle 1 of both studies using the Functional Living Index–Emesis (FLIE), a validated nausea- and vomiting-specific patient-reported outcome measure. Minimal or no impact of nausea and vomiting on patients' daily lives is defined as a FLIE total score greater than 108. In each of the 2 studies, a higher proportion of patients receiving the EMEND regimen reported minimal or no impact of nausea and vomiting on daily life (Study 1: 74% versus 64%; Study 2: 75% versus 64%).

Multiple-Cycle Extension: In the same 2 clinical studies, patients continued into the Multiple-Cycle extension for up to 5 additional cycles of chemotherapy. The proportion of patients with no emesis and no significant nausea by treatment group at each cycle is depicted in Figure 2. Antiemetic effectiveness for the patients receiving the EMEND regimen was maintained throughout repeat cycles for those patients continuing in each of the multiple cycles.

Figure 2: Proportion of Patients Receiving HEC with No Emesis and No Significant Nausea by Treatment Group and Cycle

14.2 Prevention of Nausea and Vomiting Associated with MEC in Adults

EMEND was studied in two randomized, double-blind, parallel-group studies (Studies 3 and 4) in adult patients receiving MEC.

In Study 3, in breast cancer patients, EMEND in combination with ondansetron and dexamethasone was compared with standard therapy (ondansetron and dexamethasone) in patients receiving a MEC regimen that included cyclophosphamide 750-1500 mg/m^2; or cyclophosphamide 500-1500 mg/m^2 and doxorubicin (less than or equal to 60 mg/m^2) or epirubicin (less than or equal to 100 mg/m^2). See Table 13.

In this study, the most common combinations were cyclophosphamide + doxorubicin (61%); and cyclophosphamide + epirubicin + fluorouracil (22%).

Of the 438 patients who were randomized to receive the EMEND regimen, 99.5% were women. Of these, approximately 80% were White, 8% Black, 8% Asian, 4% Hispanic, and less than 1% Other. The EMEND-treated patients in this clinical study ranged from 25 to 78 years of age, with a mean age of 53 years; 70 patients were 65 years or older, with 12 patients being over 74 years.

Table 13: MEC Treatment Regimens – Studies 3 and 4 [EMEND placebo and dexamethasone placebo were used to maintain blinding.]
 | Day 1 | Day 2 | Day 3
CINV EMEND Regimen
Oral EMEND [EMEND was administered 1 hour prior to chemotherapy treatment on Day 1 and in the mornings on Days 2 and 3.] | 125 mg | 80 mg | 80 mg
Oral Dexamethasone | 12 mg [Dexamethasone was administered 30 minutes prior to chemotherapy treatment on Day 1. The 12 mg dose of dexamethasone on Day 1 reflects a dosage adjustment to account for a drug interaction with the EMEND regimen [see Clinical Pharmacology (12.3)].] | none | none
Oral Ondansetron | 8 mg × 2 doses [The first ondansetron dose was administered 30 to 60 minutes prior to chemotherapy treatment on Day 1 and the second dose was administered 8 hours after first ondansetron dose.] | none | none
CINV Standard Therapy
Oral Dexamethasone | 20 mg | none | none
Oral Ondansetron | 8 mg × 2 doses | 8 mg twice daily | 8 mg twice daily

The antiemetic activity of EMEND was evaluated based on the following endpoints in which emetic episodes included vomiting, retching, or dry heaves:

Primary endpoint:

- complete response (defined as no emetic episodes and no use of rescue therapy as recorded in patient diaries) in the overall phase (0 to 120 hours post-chemotherapy)

Other prespecified endpoints:

- no emesis (defined as no emetic episodes regardless of use of rescue therapy)
- no nausea (maximum VAS less than 5 mm on a 0 to 100 mm scale)
- no significant nausea (maximum VAS less than 25 mm on a 0 to 100 mm scale)
- complete protection (defined as no emetic episodes, no use of rescue therapy, and a maximum nausea visual analogue scale [VAS] score less than 25 mm on a 0 to 100 mm scale)
- complete response during the acute and delayed phases.

A summary of the key results from Study 3 is shown in Table 14. In Study 3, a statistically significantly (p=0.015) higher proportion of patients receiving the EMEND regimen (51%) in Cycle 1 had a complete response (primary endpoint) during the overall phase compared with patients receiving standard therapy (42%). The difference between treatment groups was primarily driven by the "No Emesis Endpoint", a principal component of this composite primary endpoint. In addition, a higher proportion of patients receiving the EMEND regimen in Cycle 1 had a complete response during the acute (0-24 hours) and delayed (25-120 hours) phases compared with patients receiving standard therapy; however, the treatment group differences failed to reach statistical significance, after multiplicity adjustments.

Table 14: Percent of Patients Receiving MEC Responding by Treatment Group and Phase — Cycle 1 of Study 3
ENDPOINTS | EMEND Regimen (N=433) [N: Number of patients included in the primary analysis of complete response.] % | Standard Therapy (N=424) % | p-Value
PRIMARY ENDPOINT [Overall: 0 to 120 hours post-chemotherapy treatment.]
Complete Response | 51 | 42 | 0.015
OTHER PRESPECIFIED ENDPOINTS
No Emesis | 76 | 59 | NS [NS when adjusted for prespecified multiple comparisons rule; unadjusted p-value <0.001.]
No Nausea | 33 | 33 | NS
No Significant Nausea | 61 | 56 | NS
No Rescue Therapy | 59 | 56 | NS
Complete Protection | 43 | 37 | NS

Additional Patient-Reported Outcomes: In Study 3, in patients receiving MEC, the impact of nausea and vomiting on patients' daily lives was assessed in Cycle 1 using the FLIE. A higher proportion of patients receiving the EMEND regimen reported minimal or no impact on daily life (64% versus 56%). This difference between treatment groups was primarily driven by the "No Vomiting Domain" of this composite endpoint.

Multiple-Cycle Extension: In Study 3, patients receiving MEC were permitted to continue into the Multiple-Cycle extension of the study for up to 3 additional cycles of chemotherapy. The antiemetic effect for patients receiving the EMEND regimen was maintained during all cycles.

In Study 4, EMEND in combination with ondansetron and dexamethasone was compared with a standard therapy (ondansetron and dexamethasone alone) in patients receiving a MEC regimen that included any intravenous dose of oxaliplatin, carboplatin, epirubicin, idarubicin, ifosfamide, irinotecan, daunorubicin, doxorubicin; cyclophosphamide intravenous (less than 1500 mg/m^2); or cytarabine intravenous (greater than 1 g/m^2). See Table 13. Patients receiving the EMEND regimen were receiving chemotherapy for a variety of tumor types including 50% with breast cancer, 21% with gastrointestinal cancers including colorectal cancer, 13% with lung cancer and 6% with gynecological cancers.

Of the 430 patients who were randomized to receive the EMEND regimen, 76% were women and 24% were men. The distribution by race was 67% White, 6% Black or African American, 11% Asian, and 12% multiracial. Classified by ethnicity, 36% were Hispanic and 64% were non-Hispanic. The EMEND-treated patients in this clinical study ranged from 22 to 85 years of age, with a mean age of 57 years; approximately 59% of the patients were 55 years or older with 32 patients being over 74 years.

The antiemetic activity of EMEND was evaluated based on no vomiting (with or without rescue therapy) in the overall period (0 to 120 hours post-chemotherapy) and complete response (defined as no vomiting and no use of rescue therapy) in the overall period.

A summary of the key results from Study 4 is shown in Table 15. In Study 4, a statistically significantly higher proportion of patients receiving the EMEND regimen (76%) in Cycle 1 had no vomiting during the overall phase compared with patients receiving standard therapy (62%). In addition, a higher proportion of patients receiving the EMEND regimen (69%) in Cycle 1 had a complete response in the overall phase (0-120 hours) compared with patients receiving standard therapy (56%). In the acute phase (0 to 24 hours following initiation of chemotherapy), a higher proportion of patients receiving EMEND compared to patients receiving standard therapy were observed to have no vomiting (92% and 84%, respectively) and complete response (89% and 80%, respectively). In the delayed phase (25 to 120 hours following initiation of chemotherapy), a higher proportion of patients receiving EMEND compared to patients receiving standard therapy were observed to have no vomiting (78% and 67%, respectively) and complete response (71% and 61%, respectively).

In a subgroup analysis by tumor type, a numerically higher proportion of patients receiving EMEND were observed to have no vomiting and complete response compared to patients receiving standard therapy. For sex, the difference in complete response rates between the EMEND and standard regimen groups was 14% in females (64.5% and 50.3%, respectively) and 4% in males (82.2% and 78.2%, respectively) during the overall phase. A similar difference for sex was observed for the no vomiting endpoint.

Table 15: Percent of Patients Receiving MEC Responding by Treatment Group — Cycle 1 of Study 4
ENDPOINTS | EMEND Regimen (N=430) [N = Number of patients who received chemotherapy treatment, study drug, and had at least one post-treatment efficacy evaluation.] % | Standard Therapy (N=418) % | p-Value
No Vomiting Overall | 76 | 62 | <0.0001
Complete Response Overall | 69 | 56 | 0.0003

14.3 Prevention of Nausea and Vomiting Associated with HEC or MEC in Pediatric Patients

In a randomized, double-blind, active comparator-controlled clinical study that included 302 pediatric patients aged 6 months to 17 years receiving HEC or MEC, EMEND in combination with ondansetron was compared to ondansetron alone (control regimen) for the prevention of CINV (Study 5). Intravenous dexamethasone was permitted as part of the antiemetic regimen in both treatment groups, at the discretion of the physician. A 50% dose reduction of dexamethasone was required for patients in the EMEND group, reflecting a dosage adjustment to account for a drug interaction [see Clinical Pharmacology (12.3)]. No dexamethasone dose reduction was required for patients who received the control regimen.

Eligible patients had documented malignancy at either an original diagnosis or relapse and were scheduled to receive emetogenic chemotherapy or a chemotherapy regimen not previously tolerated due to vomiting along with ondansetron as part of their antiemetic regimen.

Of the 152 pediatric patients randomized to receive the EMEND regimen, 55% were male, 45% female, 78% White, 7% Asian, 0% Black, 24% Hispanic, and 13% Multi-Racial. The most common primary malignancies in subjects receiving the EMEND regimen were osteosarcoma (11%), Ewing's sarcoma (11%), neuroblastoma (9%) and rhabdomyosarcoma (8%). Other concomitant chemotherapy agents commonly administered and the number of EMEND patients exposed were: vincristine sulfate (65), etoposide (59), doxorubicin (48), ifosfamide (45), carboplatin (39), and cisplatin (35).

The treatment regimens in Study 5 for pediatric patients are defined in Table 16. Of the pediatric patients, 29% in the EMEND regimen and 28% in the control regimen used dexamethasone as part of the antiemetic regimen in Cycle 1.

Table 16: HEC and MEC Treatment Regimens [Intravenous dexamethasone was permitted at the discretion of the physician. A 50% dose reduction of dexamethasone was required for patients in the EMEND group, reflecting a dosage adjustment to account for a drug interaction [see Clinical Pharmacology (12.3)]. No dexamethasone dose reduction was required for patients in the control regimen.] for Pediatric Patients 6 Months to 17 Years of Age— Study 5
 | Day 1 | Day 2 | Day 3
CINV EMEND Regimen
Pediatric Patients 6 Months to less than 12 Years of Age [EMEND was administered 1 hour prior to chemotherapy treatment on Days 1, 2, and 3. If no chemotherapy was given on Days 2 and 3, EMEND was administered in the morning.] | 3 mg/kg body weight oral suspension | 2 mg/kg body weight oral suspension | 2 mg/kg body weight oral suspension
Pediatric Patients 12 to 17 Years of Age | 125 mg capsule | 80 mg capsule | 80 mg capsule
Ondansetron | Per standard of care [Ondansetron was administered 30 minutes prior to chemotherapy on Day 1] | none | none
CINV Control Regimen [EMEND placebo was used to maintain blinding.]
Ondansetron | Per standard of care | none | none

The antiemetic activity of EMEND was evaluated over a 5-day (120 hour) period following the initiation of chemotherapy on Day 1. The primary endpoint in Study 5 was complete response in the delayed phase (25 to 120 hours following chemotherapy) in Cycle 1. Patients had the opportunity to receive open-label EMEND in subsequent cycles (Optional Cycles 2-6); however, efficacy was not assessed in these optional cycles. Overall efficacy was based on the evaluation of the following endpoints:

Primary endpoint:

- complete response (no vomiting, retching and no use of rescue medication) in the delayed phase (25 to 120 hours following initiation of chemotherapy)

Other prespecified endpoints:

- complete response in the acute phase (0 to 24 hours following initiation of chemotherapy)
- complete response in the overall phase (up to 120 hours following initiation of chemotherapy)
- no vomiting (defined as no emesis, retching or dry heaves, regardless of use of rescue medication) in the overall phase
- safety and tolerability

A summary of the key study results is shown in Table 17.

Table 17: Percent of Patients Who Responded to Treatment by Treatment Group and Phase – Cycle 1 of Study 5
 | EMEND Regimen n/m (%) | Control Regimen n/m (%)
PRIMARY ENDPOINT
Complete Response [Complete Response = No vomiting or retching and no use of rescue medication.] - Delayed phase | 77/152 (50.7) [p<0.01 when compared to Control Regimen] | 39/150 (26.0)
OTHER PRESPECIFIED ENDPOINTS
Complete Response – Acute phase | 101/152 (66.4) [p<0.05 when compared to Control Regimen] | 78/150 (52.0)
Complete Response – Overall phase | 61/152 (40.1) | 30/150 (20.0)
n/m = Number of patients with desired response/number of patients included in time point.
Acute Phase: 0 to 24 hours following initiation of chemotherapy.
Delayed Phase: 25 to 120 hours following initiation of chemotherapy.
Overall Phase: 0 to 120 hours following initiation of chemotherapy.

16 HOW SUPPLIED/STORAGE AND HANDLING

80-mg capsules: White, opaque, hard gelatin capsule with "461" and "80 mg" printed radially in black ink on the body. They are supplied as follows:

NDC 0006-0461-02 unit-of-use BiPack of 2

Unit-of-use TriPack containing one 125-mg capsule and two 80-mg capsules. 125 mg-capsules: Opaque, hard gelatin capsule with white body and pink cap with “462” and “125 mg” printed radially in black ink on the body. 80-mg capsules: White, opaque, hard gelatin capsule with “461” and “80 mg” printed radially in black ink on the body.

NDC 0006-3862-03.

125 mg for oral suspension: Pink to light pink powder, in a single-use pouch, packaged as a kit with one 1 mL oral dosing dispenser, one 5 mL oral dosing dispenser, one cap and one mixing cup. It is supplied as follows:

NDC 0006-3066-03 – unit of use carton.

Storage and Handling

Capsules

Store at 20-25°C (68-77°F) [see USP Controlled Room Temperature].

For Oral Suspension

Store unopened pouch at 20-25°C (68-77°F); excursions permitted between 15-30°C (between 59-86°F). Store in the original container. Do not open pouch until ready for use.

Once prepared, if suspension is not used immediately, store refrigerated [between 36°F-46°F (2°C-8°C)] for up to 72 hours prior to use. When ready to use, the mixture can be kept at room temperature [between 68°F-77°F (20°C-25°C)] for up to 3 hours.

17 PATIENT COUNSELING INFORMATION

Advise the patient to read the FDA-approved patient labeling (Patient Information).

Hypersensitivity Reactions

Advise patients that hypersensitivity reactions, including anaphylaxis, have been reported in patients taking EMEND. Advise patients to stop taking EMEND and seek immediate medical attention if they experience signs or symptoms of a hypersensitivity reaction, such as hives, rash and itching, skin peeling or sores, or difficulty in breathing or swallowing.

Drug Interactions

Advise patients to discuss all medications they are taking, including other prescription, non-prescription medication or herbal products [see Contraindications (4), Warnings and Precautions (5.1)].

Warfarin: Instruct patients on chronic warfarin therapy to follow instructions from their healthcare provider regarding blood draws to monitor their INR during the 2-week period, particularly at 7 to 10 days, following initiation of the 3-day regimen of EMEND with each chemotherapy cycle [see Warnings and Precautions (5.2)].

Hormonal Contraceptives: Advise patients that administration of EMEND may reduce the efficacy of hormonal contraceptives. Instruct patients to use effective alternative or back-up methods of contraception (such as condoms and spermicides) during treatment with EMEND and for 1 month following the last dose of EMEND [see Warnings and Precautions (5.3), Use in Specific Populations (8.3)].

Distributed by:
Merck Sharp & Dohme LLC, Rahway, NJ 07065, USA

For patent information: www.msd.com/research/patent

Copyright © 2003-2022 Merck & Co., Inc., Rahway, NJ, USA, and its affiliates.
All rights reserved.

uspi-mk0869-mf-2205r017

Patient Information
EMEND® (EE mend)
(aprepitant)
capsules
EMEND® (EE mend)
(aprepitant)
for oral suspension

Read this Patient Information before you start taking EMEND and each time you get a refill. There may be new information. This information does not take the place of talking with your healthcare provider about your medical condition or treatment.

What is EMEND?

EMEND for oral suspension is a prescription medicine used:

- with other medicines that treat nausea and vomiting in patients 6 months of age and older to prevent nausea and vomiting caused by certain anti-cancer (chemotherapy) medicines

EMEND capsules is a prescription medicine used:

- with other medicines that treat nausea and vomiting in patients 12 years of age and older to prevent nausea and vomiting caused by certain anti-cancer (chemotherapy) medicines

EMEND is not used to treat nausea and vomiting that you already have.

EMEND should not be used continuously for a long time (chronic use).

Who should not take EMEND?

Do not take EMEND if you:

- are allergic to aprepitant or any of the ingredients in EMEND. See the end of this leaflet for a complete list of ingredients in EMEND.
- are taking pimozide (ORAP®)

What should I tell my healthcare provider before taking EMEND?

Before you take EMEND, tell your healthcare provider if you:

- have liver problems
- are pregnant or plan to become pregnant. It is not known if EMEND can harm your unborn baby.
  - Women who use birth control medicines containing hormones to prevent pregnancy (birth control pills, skin patches, implants, and certain IUDs) should also use a back-up method of birth control that does not contain hormones, such as condoms and spermicides, during treatment with EMEND and for 1 month after your last dose of EMEND.
- are breastfeeding or plan to breastfeed. It is not known if EMEND passes into your breast milk. Talk to your healthcare provider about the best way to feed your baby if you take EMEND.

Tell your healthcare provider about all the medicines you take, including prescription and over-the-counter medicines, vitamins, and herbal supplements.

EMEND may affect the way other medicines work, and other medicines may affect how EMEND works causing serious side effects.

Know the medicines you take. Keep a list of them to show your healthcare provider or pharmacist when you get a new medicine.

How should I take EMEND?

- Take EMEND exactly as prescribed.
- Swallow EMEND capsules whole.
- EMEND may be taken with or without food.
- If you take too much EMEND, call your healthcare provider, or go to the nearest hospital emergency room.
- EMEND is taken as 3 doses over 3 days - starting on the day you have chemotherapy, and for the following 2 days.
- In adults, there are 2 ways your healthcare provider may prescribe EMEND for you:
  1. Capsules of EMEND by mouth for all 3 doses:
    - You should get a package that has 3 capsules of EMEND.
    - Day 1 (Day of chemotherapy): Take one 125 mg capsule of EMEND (white and pink) by mouth 1 hour before you start your chemotherapy treatment.
    - Day 2 and Day 3: Take one 80 mg capsule of EMEND (white) by mouth 1 hour before you start your chemotherapy treatment. If no chemotherapy treatment is given on Days 2 and 3, EMEND should be taken in the morning.
  2. Oral suspension of EMEND by mouth for all 3 doses, for adults who are not able to swallow capsules:
    - For each dose of EMEND for oral suspension, you will get a pre-filled oral dosing dispenser that contains your prescribed dose.
    - See the detailed Instructions for Use that comes with EMEND for oral suspension for information about the correct way to take a dose of EMEND for oral suspension. If you have questions about how to take EMEND for oral suspension, talk to your healthcare provider.
    - Day 1 (Day of chemotherapy): Take 1 dose of EMEND for oral suspension by mouth 1 hour before you start your chemotherapy treatment.
    - Day 2 and Day 3: Take 1 dose of EMEND for oral suspension by mouth 1 hour before you start your chemotherapy treatment. If no chemotherapy treatment is given on Days 2 and 3, EMEND for oral suspension should be taken in the morning.
- In children 12 years of age and older who can swallow capsules by mouth, EMEND is prescribed as capsules of EMEND by mouth for all 3 doses:
  - You should get a package that has 3 capsules of EMEND.
  - Day 1 (Day of chemotherapy): Take one 125 mg capsule of EMEND (white and pink) by mouth 1 hour before you start your chemotherapy treatment.
  - Day 2 and Day 3: Take one 80 mg capsule of EMEND (white) by mouth 1 hour before you start your chemotherapy treatment. If no chemotherapy treatment is given on Days 2 and 3, EMEND should be taken in the morning.
- In children 6 months to less than 12 years of age or in children 12 years of age and older who are not able to swallow capsules, EMEND is prescribed as oral suspension of EMEND by mouth for all 3 doses:
  - For each dose of EMEND, you will get a pre-filled oral dosing dispenser that contains your child's prescribed dose.
  - See the detailed Instructions for Use that comes with EMEND for oral suspension, for information about the correct way to give a dose of EMEND for oral suspension. If you have questions about how to give EMEND for oral suspension, talk to your child's healthcare provider.
  - Day 1 (Day of chemotherapy): Give 1 dose of EMEND for oral suspension to your child by mouth 1 hour before they start their chemotherapy treatment.
  - Day 2 and Day 3: Give 1 dose of EMEND for oral suspension to your child by mouth 1 hour before they start their chemotherapy treatment. If no chemotherapy treatment is given on Days 2 and 3, EMEND should be given in the morning.
- If you take the blood thinner medicine warfarin sodium (COUMADIN®, JANTOVEN®), your healthcare provider may do blood tests after you take EMEND to check your blood clotting.

What are the possible side effects of EMEND?

- In adults taking EMEND, the most common side effects include tiredness, diarrhea, weakness, indigestion, stomach (abdominal) pain, hiccups, decrease in white blood cell count, dehydration, and changes in liver function tests.
- In children 6 months to 17 years of age, the most common side effects include decrease in white blood cell count, headache, diarrhea, decreased appetite, cough, tiredness, decrease in red blood cell count, dizziness, and hiccups.

Tell your healthcare provider if you have any side effect that bothers you or that does not go away. These are not all of the possible side effects of EMEND. For more information ask your healthcare provider or pharmacist.

Call your healthcare provider for medical advice about side effects. You may report side effects to FDA at 1-800-FDA-1088.

How should I store EMEND?

EMEND capsules

- Store EMEND capsules at room temperature, between 68°F to 77°F (20°C to 25°C).

EMEND for oral suspension

- Store EMEND for oral suspension in the refrigerator, between 36°F to 46°F (2°C to 8°C).
- Use EMEND for oral suspension within 2 days of getting the medicine from your healthcare provider.
- When ready to use, EMEND for oral suspension can be kept at room temperature, between 68°F to 77°F (20°C to 25°C) for up to 3 hours.

Keep EMEND and all medicines out of the reach of children.

General information about the safe and effective use of EMEND

Medicines are sometimes prescribed for purposes other than those listed in a Patient Information leaflet. Do not use EMEND for a condition for which it was not prescribed. Do not give EMEND to other people, even if they have the same symptoms you have. It may harm them. You can ask your healthcare provider or pharmacist for information about EMEND that is written for health professionals. For more information about EMEND call 1-800-622-4477 or go to www.emend.com.

What are the ingredients in EMEND?

EMEND capsules:

Active ingredient: aprepitant

Inactive ingredients: sucrose, microcrystalline cellulose, hydroxypropyl cellulose and sodium lauryl sulfate. The capsule shell excipients are gelatin, titanium dioxide, and may contain sodium lauryl sulfate and silicon dioxide. The 125 mg capsule shell also contains red ferric oxide and yellow ferric oxide.

EMEND for oral suspension:

Active ingredient: aprepitant

Inactive ingredients: sucrose, lactose, hydroxypropyl cellulose, sodium lauryl sulfate, red iron oxide, and sodium stearyl fumarate.

Distributed by: Merck Sharp & Dohme LLC, Rahway, NJ 07065, USA
For patent information: www.msd.com/research/patent
The brands listed in the above sections "Who should not take EMEND?" and "How should I take EMEND?" are the registered trademarks of their respective owners and are not trademarks of Merck Sharp & Dohme LLC.
Copyright © 2003-2022 Merck & Co., Inc., Rahway, NJ, USA, and its affiliates.
All rights reserved.
usppi-mk0869-mf-2205r008

This Patient Information has been approved by the U.S. Food and Drug Administration.

Revised: May 2022

Instructions for Use

EMEND® (EE-mend)
(aprepitant)
for oral suspension

Read the Patient Information and Instructions for
Use for EMEND for oral suspension before you take or
before you give a dose to your child

Take by mouth only

How to give a dose of EMEND for oral suspension

The healthcare provider has prepared the dose of EMEND for you or your child.

1. You will get EMEND in an oral dosing dispenser

2. Keep the oral dosing dispenser in the refrigerator until you give EMEND to yourself or your child

- Store EMEND in the refrigerator between 36°F to 46°F (2°C to 8°C).
- Use EMEND within 2 days of getting the medicine from the healthcare provider.
- When ready to use, EMEND can be kept at room temperature, between 68°F to 77°F (20°C to 25°C) for up to 3 hours.
- Keep EMEND and all medicines out of the reach of children.

3. Give EMEND

4. Throw away the oral dosing dispenser and cap

The color of the medicine in the oral dosing dispenser may be different shades of pink (light pink to dark pink). This is normal and the medicine is okay to use.

- Take the cap off the oral dosing dispenser.
- Place the tip of the oral dosing dispenser in your mouth or in your child's mouth along the inner cheek on either the right or left side.
- Slowly push the plunger all the way down to give all of the medicine in the oral dosing dispenser.

Call the healthcare provider if you or your child is not able to take the prescribed dose.

For more information go to www.emend.com or call 1-800-622-4477.
This Instructions for Use has been approved by the U.S. Food and Drug Administration.
Distributed by:
Merck Sharp & Dohme LLC, Rahway, NJ 07065, USA
For patent information: www.msd.com/research/patent
Copyright © 2015-2022 Merck & Co., Inc., Rahway, NJ, USA, and its affiliates.
All rights reserved.
Issued: 05/2022
usifu-mk0869-mf-2205r001

PRINCIPAL DISPLAY PANEL - 80 mg Capsule Dose Pack

NDC 0006-0461-02

BiPack
2 capsules

EMEND®
(aprepitant) capsules

80 mg

For Adults and
Pediatric Patients
12 years of Age and Older

You have already been given
a capsule of EMEND (aprepitant) to
prevent nausea and vomiting before
your chemotherapy on Day 1.

The two capsules in this package
are to be taken on Days 2 and 3.

Each capsule contains 80 mg
of aprepitant.

USUAL DOSAGE:
See accompanying circular.

Rx only

Keep this and all drugs out of
the reach of children.

Dist. by: Merck Sharp & Dohme LLC
Rahway, NJ 07065, USA
Manuf. by: Alkermes Pharma Ireland Limited, Athlone, Ireland
Aprepitant (active ingred.) Made in Switzerland.
Formulated in Ireland.

PRINCIPAL DISPLAY PANEL - 125 mg Capsule Carton

NDC 0006-0462-06

125 mg

EMEND®
(APREPITANT) CAPSULES

For Adults and
Pediatric Patients
12 years of Age and Older

Each capsule contains 125 mg aprepitant.

Store at 20-25°C (68-77°F) [see USP Controlled Room Temperature].
USUAL DOSAGE: See accompanying circular.

Rx only

This is a bulk package and not intended for dispensing.
Package not child resistant.

6 capsules

PRINCIPAL DISPLAY PANEL - 3 Capsule Kit Carton

NDC 0006-3862-03

TriPack
3 capsules

EMEND®
(aprepitant) capsules

125 mg 80 mg

For Adults and
Pediatric Patients
12 years of Age and Older

One 125-mg capsule contains
125 mg aprepitant.

Two 80-mg capsules each containing
80 mg of aprepitant.

USUAL DOSAGE:
See accompanying circular.

Rx only

Keep this and all drugs out of
the reach of children.

Dist. by: Merck Sharp & Dohme LLC
Rahway, NJ 07065, USA
Manuf. by: Alkermes Pharma Ireland Limited, Athlone, Ireland
Aprepitant (active ingred.) Made in Switzerland.
Formulated in Ireland.

PRINCIPAL DISPLAY PANEL - 40 mg Capsule Carton

NDC 0006-0464-10

40 mg

EMEND®
(APREPITANT) CAPSULE

Each capsule contains 40 mg aprepitant.
Rx only

Package not child resistant. Keep this
and all drugs out of the reach of children.

Dist. by: Merck Sharp & Dohme Corp., a subsidiary of
MERCK & CO., INC., Whitehouse Station, NJ 08889, USA
Manuf. by: Alkermes Pharma Ireland Limited, Athlone, Ireland
Formulated in Ireland

1 Capsule

PRINCIPAL DISPLAY PANEL - Kit Carton

NDC 0006-3066-03

EMEND®
(aprepitant)
for oral
suspension

125 mg

Single-Dose Kit

Discard Unused Portion

This product must be
reconstituted and dose
must be measured by a
healthcare provider.

See package insert and
accompanying directions.

For Oral
Administration Only

Rx only